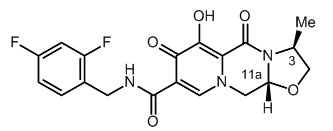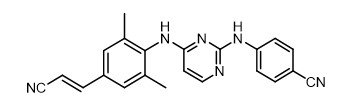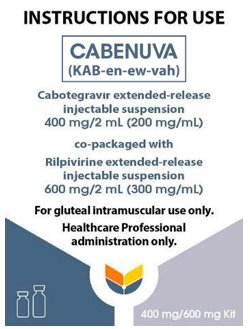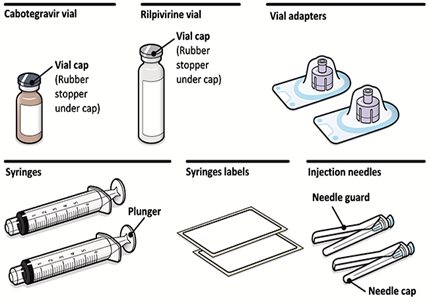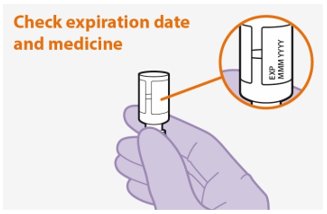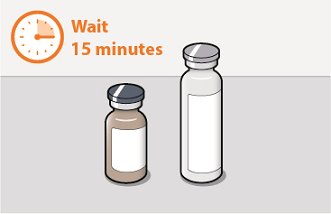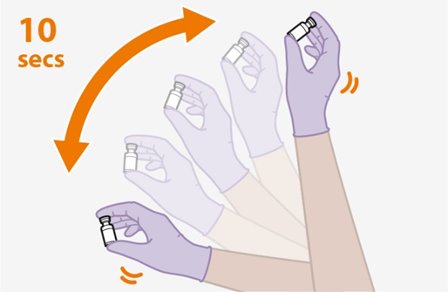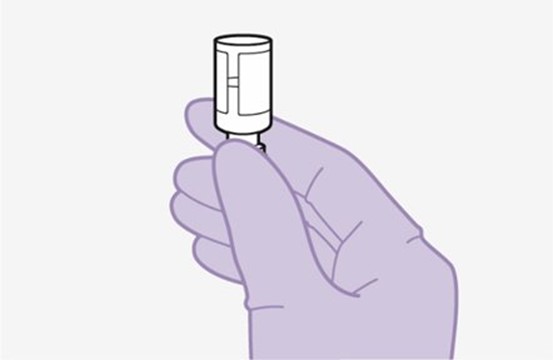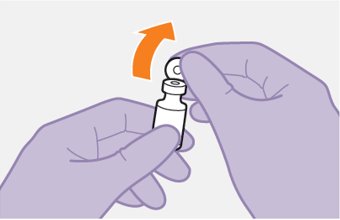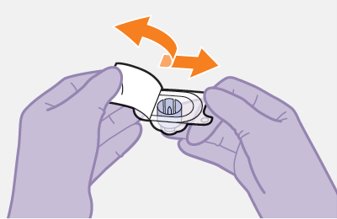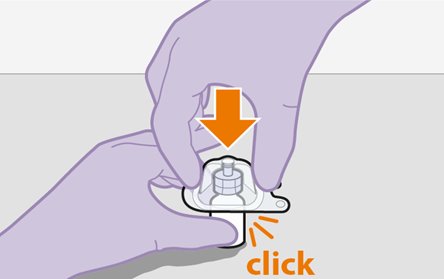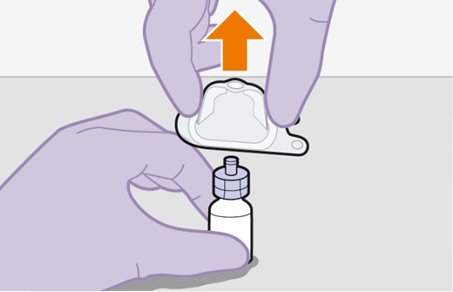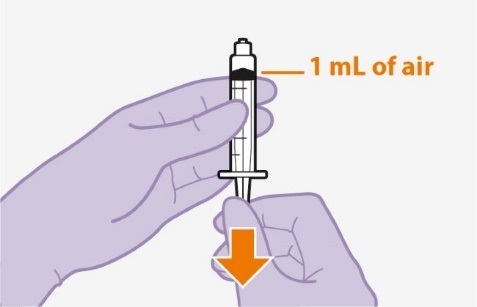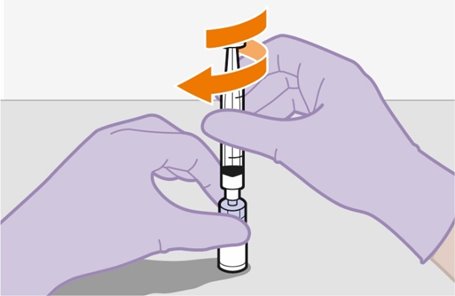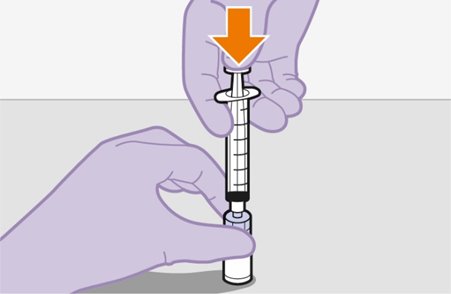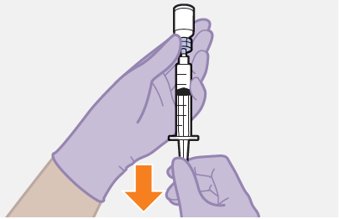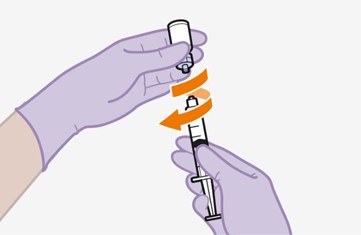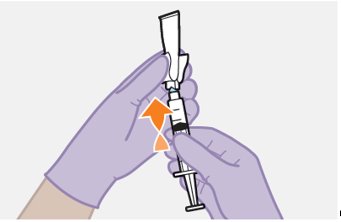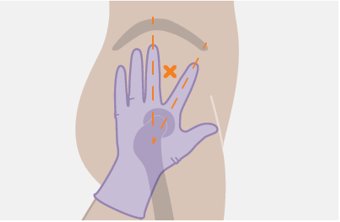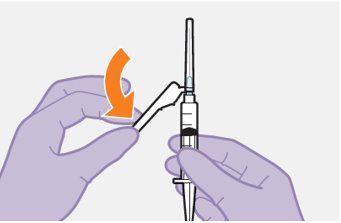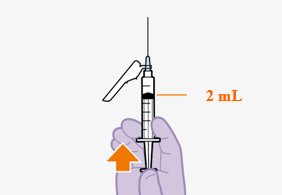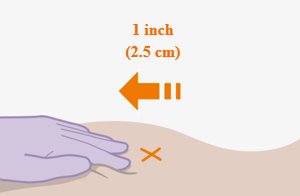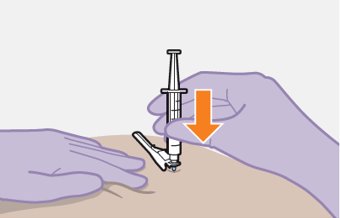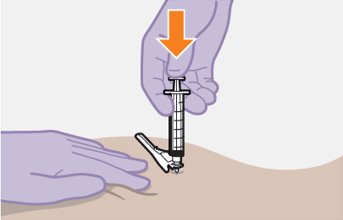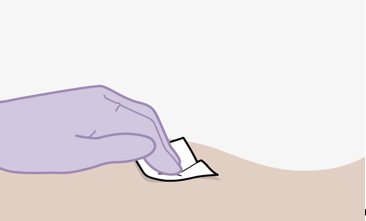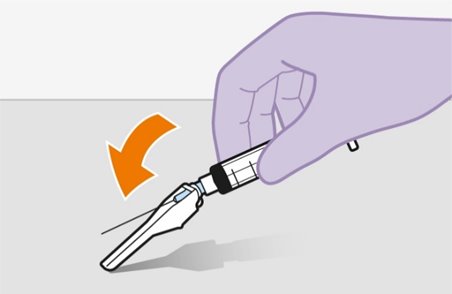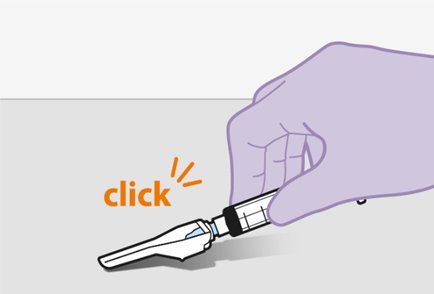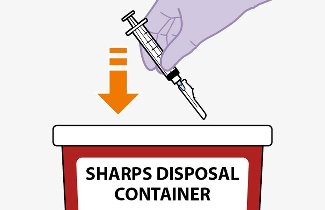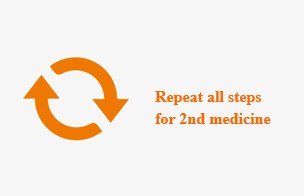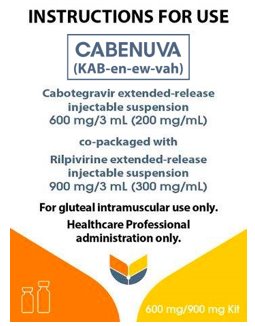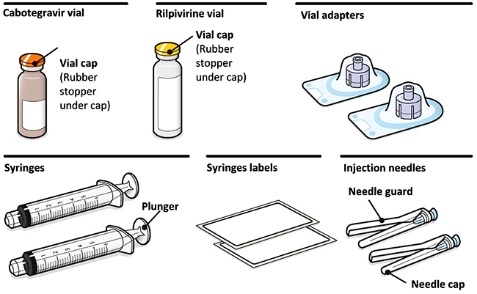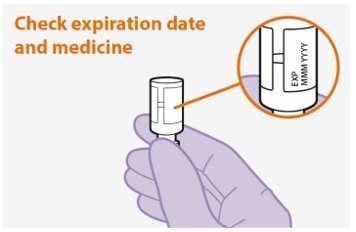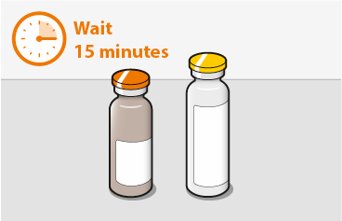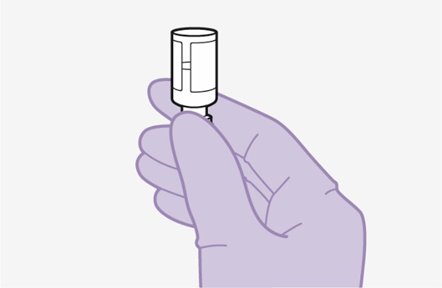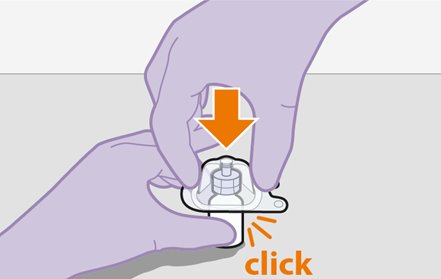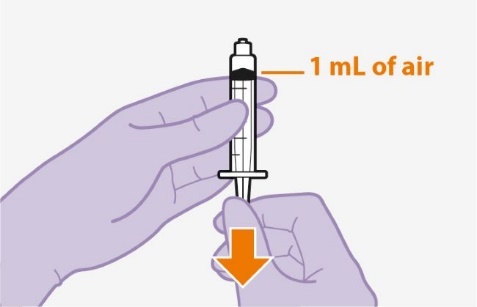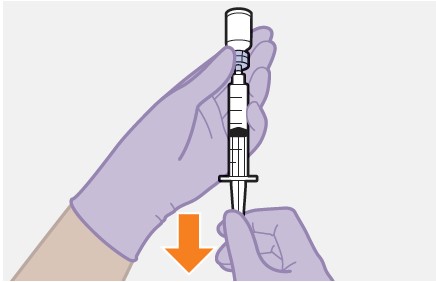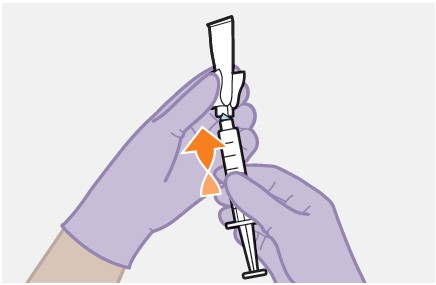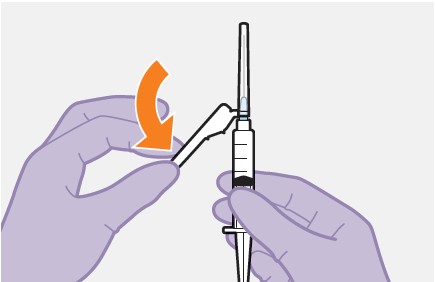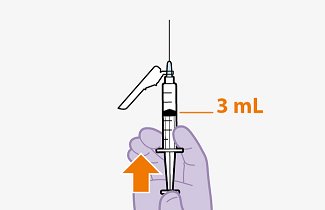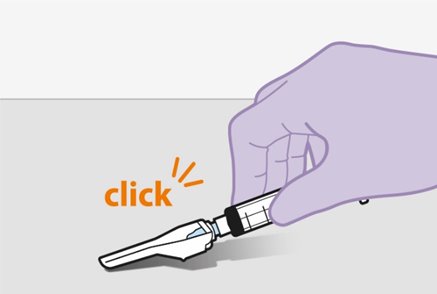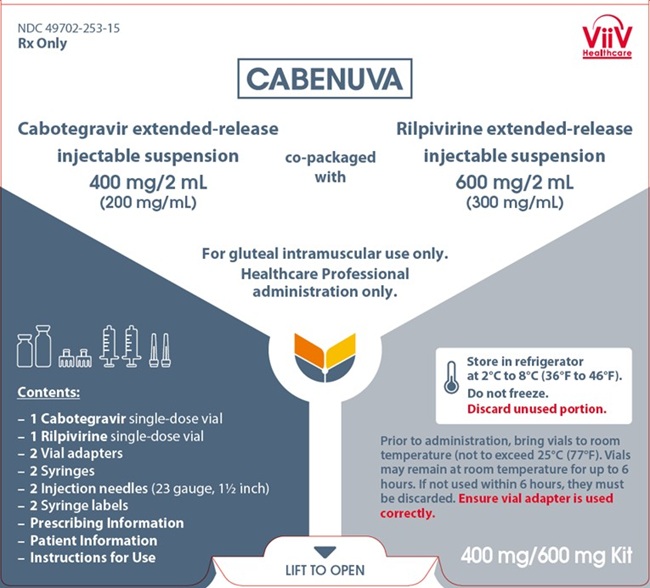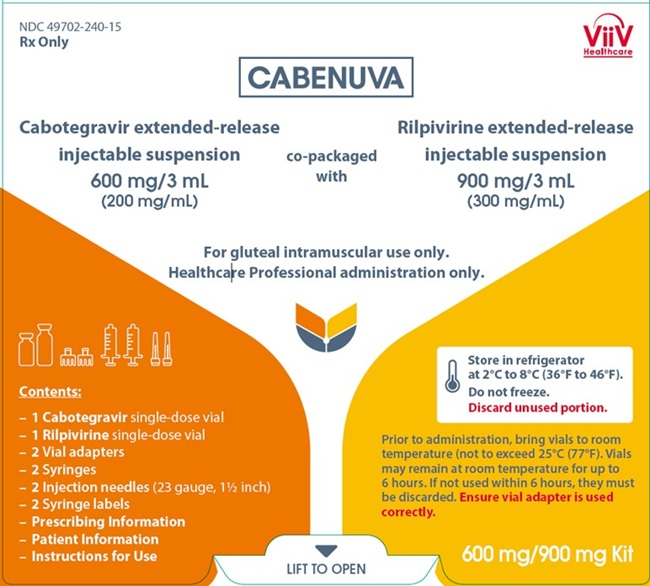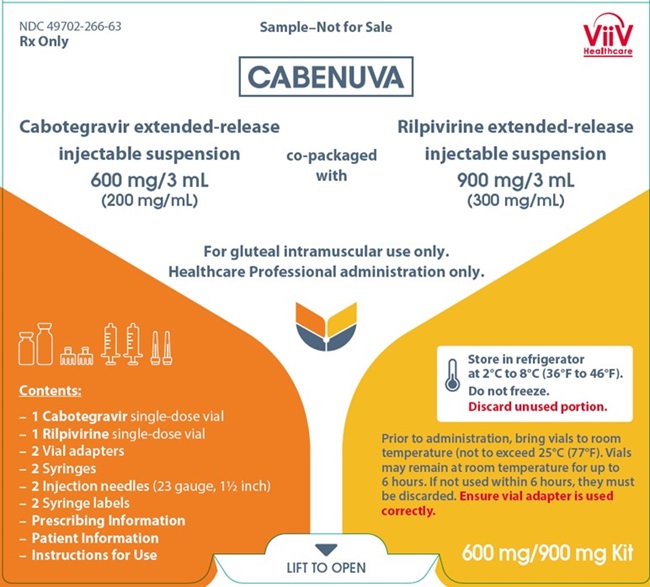 DRUG LABEL: Cabenuva
NDC: 49702-253 | Form: KIT | Route: INTRAMUSCULAR
Manufacturer: ViiV Healthcare Company
Category: prescription | Type: HUMAN PRESCRIPTION DRUG LABEL
Date: 20251126

ACTIVE INGREDIENTS: CABOTEGRAVIR 200 mg/1 mL; RILPIVIRINE 300 mg/1 mL
INACTIVE INGREDIENTS: MANNITOL; POLYSORBATE 20; POLYETHYLENE GLYCOL 3350; WATER; POLOXAMER 338; CITRIC ACID MONOHYDRATE; DEXTROSE MONOHYDRATE; SODIUM PHOSPHATE, MONOBASIC, MONOHYDRATE; SODIUM HYDROXIDE; WATER

HIGHLIGHTS OF PRESCRIBING INFORMATION

These highlights do not include all the information needed to use CABENUVA safely and effectively. See full prescribing information for CABENUVA.
CABENUVA (cabotegravir extended-release injectable suspension; rilpivirine extended-release injectable suspension), co-packaged for intramuscular use
Initial U.S. Approval: 2021

RECENT MAJOR CHANGES

Warnings and Precautions, Hypersensitivity Reactions (5.1) | 4/2025

1 INDICATIONS AND USAGE

CABENUVA, a 2-drug co-packaged product of cabotegravir, an HIV-1 integrase strand transfer inhibitor (INSTI), and rilpivirine, an HIV-1 non‑nucleoside reverse transcriptase inhibitor (NNRTI), is indicated as a complete regimen for the treatment of HIV-1 infection in adults and adolescents 12 years of age and older and weighing at least 35 kg to replace the current antiretroviral regimen in those who are virologically suppressed (HIV‑1 RNA <50 copies/mL) on a stable antiretroviral regimen with no history of treatment failure and with no known or suspected resistance to either cabotegravir or rilpivirine. (1)

2 DOSAGE AND ADMINISTRATION

- Refer to full prescribing information for detailed information on dosage and administration recommendations. (2)
- Prior to initiating treatment with CABENUVA, oral lead-in dosing may be considered to assess the tolerability of cabotegravir and rilpivirine with the recommended dosage used for approximately 1 month. (2.3)
- For gluteal intramuscular injection only. (2.4, 2.5, 2.9)
- Recommended Monthly Dosing Schedule: Initiate injections of CABENUVA (600 mg of cabotegravir and 900 mg of rilpivirine) on the last day of current antiretroviral therapy or oral lead-in and continue with injections of CABENUVA (400 mg of cabotegravir and 600 mg of rilpivirine) every month thereafter. (2.4)
- Recommended Every-2-Month Dosing Schedule: Initiate injections of CABENUVA (600 mg of cabotegravir and 900 mg of rilpivirine) on the last day of current antiretroviral therapy or oral lead-in for 2 consecutive months and continue with injections of CABENUVA every 2 months thereafter. (2.5)

3 DOSAGE FORMS AND STRENGTHS

Injection:

- Kit of single-dose vials of 400 mg/2 mL (200 mg/mL) of cabotegravir extended-release injectable suspension and 600 mg/2 mL (300 mg/mL) of rilpivirine extended-release injectable suspension. (3)
- Kit of single-dose vials of 600 mg/3 mL (200 mg/mL) of cabotegravir extended-release injectable suspension and 900 mg/3 mL (300 mg/mL) of rilpivirine extended-release injectable suspension. (3)

4 CONTRAINDICATIONS

- Previous hypersensitivity reaction to cabotegravir or rilpivirine. (4)
- Coadministration with drugs where significant decreases in cabotegravir and/or rilpivirine plasma concentrations may occur, which may result in loss of virologic response. (4)

5 WARNINGS AND PRECAUTIONS

- Serious or severe hypersensitivity reactions have been reported with cabotegravir- and rilpivirine-containing regimens. Reactions associated with cabotegravir include Stevens-Johnson syndrome (SJS)/toxic epidermal necrolysis (TEN). Reactions associated with rilpivirine-containing regimens include cases of drug reaction with eosinophilia and systemic symptoms (DRESS). Discontinue CABENUVA immediately if signs or symptoms of hypersensitivity reactions develop. (5.1)
- Serious post-injection reactions with rilpivirine were reported. Monitor and treat as clinically indicated. (5.2)
- Hepatotoxicity has been reported in patients receiving cabotegravir or rilpivirine. Monitoring of liver chemistries is recommended. Discontinue CABENUVA if hepatotoxicity is suspected. (5.3)
- Depressive disorders have been reported with CABENUVA. Prompt evaluation is recommended for depressive symptoms. (5.4)
- Residual concentrations of cabotegravir and rilpivirine may remain in the systemic circulation of patients up to 12 months or longer. It is essential to initiate an alternative, fully suppressive antiretroviral regimen no later than 1 month after the final injections of CABENUVA when dosed monthly and no later than 2 months after the final injections when dosed every 2 months. If virologic failure is suspected, prescribe an alternative regimen as soon as possible. (5.6)

6 ADVERSE REACTIONS

The most common adverse reactions (Grades 1 to 4) observed in ≥2% of participants receiving CABENUVA were injection site reactions, pyrexia, fatigue, headache, musculoskeletal pain, nausea, sleep disorders, dizziness, and rash. (6.1)

To report SUSPECTED ADVERSE REACTIONS, contact ViiV Healthcare at 1-877-844-8872 or FDA at 1-800-FDA-1088 or www.fda.gov/medwatch.

7 DRUG INTERACTIONS

- Refer to the full prescribing information for important drug interactions with CABENUVA. (4, 5.5, 7)
- Because CABENUVA is a complete regimen, coadministration with other antiretroviral medications for the treatment of HIV-1 infection is not recommended. (7.1)
- Drugs that induce uridine diphosphate glucuronosyltransferase (UGT)1A1 or cytochrome P450 (CYP)3A4 may decrease the plasma concentrations of the components of CABENUVA. (4, 7.3, 7.4)
- CABENUVA should be used with caution in combination with drugs with a known risk of Torsade de Pointes. (7.3, 7.4)

8 USE IN SPECIFIC POPULATIONS

- Pregnancy: After oral use of rilpivirine, exposures were generally lower during pregnancy compared with the postpartum period. (8.1)

FULL PRESCRIBING INFORMATION

1 INDICATIONS AND USAGE

CABENUVA is indicated as a complete regimen for the treatment of HIV-1 infection in adults and adolescents 12 years of age and older and weighing at least 35 kg to replace the current antiretroviral regimen in those who are virologically suppressed (HIV-1 RNA <50 copies/mL) on a stable antiretroviral regimen with no history of treatment failure and with no known or suspected resistance to either cabotegravir or rilpivirine [see Microbiology (12.4), Clinical Studies (14.1)].

2 DOSAGE AND ADMINISTRATION

2.1 Dosage and Administration Overview

- CABENUVA contains cabotegravir extended-release injectable suspension in a single-dose vial and rilpivirine extended-release injectable suspension in a single-dose vial [see Dosage Forms and Strengths (3)].
- CABENUVA must be administered by a healthcare provider by gluteal intramuscular injection [see Dosage and Administration (2.9)].
- CABENUVA may be initiated with oral cabotegravir and oral rilpivirine prior to the intramuscular injections or the patient may proceed directly to injection of CABENUVA without an oral lead-in [see Dosage and Administration (2.3)].
- CABENUVA can be injected monthly or every 2 months [see Dosage and Administration (2.4, 2.5)]. Healthcare providers should discuss these 2 dosing options with the patient prior to starting CABENUVA and decide which injection dosing frequency would be the most appropriate option for the patient [see Adverse Reactions (6.1), Microbiology (12.4), Clinical Studies (14.1)].

2.2 Adherence to CABENUVA

Prior to starting CABENUVA, healthcare providers should carefully select patients who agree to the required monthly or every‑2-month injection dosing schedule and counsel patients about the importance of adherence to scheduled dosing visits to help maintain viral suppression and reduce the risk of viral rebound and potential development of resistance with missed doses [see Dosage and Administration (2.1), Warnings and Precautions (5.6), Microbiology (12.4)].

2.3 Optional Oral Lead-In Dosing to Assess Tolerability of CABENUVA in Adults and Adolescents 12 Years of Age and Older and Weighing at Least 35 kg

The healthcare provider and patient may decide to use an oral lead-in with oral cabotegravir and oral rilpivirine prior to the initiation of CABENUVA to assess the tolerability of cabotegravir and rilpivirine, or the healthcare provider and patient may proceed directly to injection of CABENUVA without the use of an oral lead-in.

If oral lead-in is used, the recommended oral lead-in daily dose is one 30-mg tablet of VOCABRIA (cabotegravir) and one 25-mg tablet of EDURANT (rilpivirine) taken with a meal for approximately 1 month (at least 28 days), followed by intramuscular initiation injections of CABENUVA. See Tables 1 and 2 for recommended oral lead-in and monthly or every-2-month intramuscular injection dosing schedule for CABENUVA [see Dosage and Administration (2.4, 2.5)].

2.4 Recommended Monthly Gluteal Intramuscular Injection Dosing with CABENUVA in Adults and Adolescents 12 Years of Age and Older and Weighing at Least 35 kg

Initiation Injections (CABENUVA 600-mg/900-mg Kit)

Initiate injections on the last day of current antiretroviral therapy or oral lead-in, if used [see Dosage and Administration (2.3)]. The recommended initiation injection doses of CABENUVA are a single 600-mg (3-mL) intramuscular injection of cabotegravir and a single 900-mg (3-mL) intramuscular injection of rilpivirine. Administer cabotegravir and rilpivirine at separate gluteal injection sites (on opposite sides or at least 2 cm apart) during the same visit [see Dosage and Administration (2.9)]. Continuation injections should be initiated a month after the initiation injections.

Continuation Injections (CABENUVA 400-mg/600-mg Kit)

After the initiation injections, the recommended monthly continuation injection doses of CABENUVA are a single 400-mg (2-mL) intramuscular injection of cabotegravir and a single 600-mg (2-mL) intramuscular injection of rilpivirine at each visit (Table 1). Administer cabotegravir and rilpivirine at separate gluteal injection sites (on opposite sides or at least 2 cm apart) during the same visit [see Dosage and Administration (2.9)]. Patients may be given CABENUVA up to 7 days before or after the date the patient is scheduled to receive monthly injections.

Table 1. Recommended Dosing Schedule with Optional Oral Lead-In or Direct to Injection for Monthly Injection
Drug | Optional Oral Lead-Ina (at Least 28 Days) | Intramuscular (Gluteal) Initiation Injections (One-Time Dosing) | Intramuscular (Gluteal) Continuation Injections (Once-Monthly Dosing)
Drug | Month (at Least 28 Days) Prior to Starting Injections | Initiate Injections at Month 1b | One Month after Initiation Injection and Monthly Onwards
Cabotegravir | 30 mg once daily with a meal | 600 mg (3 mL) | 400 mg (2 mL)
Rilpivirine | 25 mg once daily with a meal | 900 mg (3 mL) | 600 mg (2 mL)
a The optional oral therapy should be continued until the day the first injection is administered.
b Given on the last day of current antiretroviral therapy or oral lead-in if used.

2.5 Recommended Every-2-Month Gluteal Intramuscular Injection Dosing with CABENUVA in Adults and Adolescents 12 Years of Age and Older and Weighing at Least 35 kg

Initiation Injections (CABENUVA 600-mg/900-mg Kit)

Initiate injections on the last day of current antiretroviral therapy or oral lead-in, if used [see Dosage and Administration (2.3)]. The recommended initiation injection doses of CABENUVA are a single 600-mg (3-mL) intramuscular injection of cabotegravir and a single 900-mg (3-mL) intramuscular injection of rilpivirine 1 month apart for 2 consecutive months (Table 2). Administer cabotegravir and rilpivirine at separate gluteal injection sites (on opposite sides or at least 2 cm apart) during the same visit [see Dosage and Administration (2.9)]. Patients may be given CABENUVA up to 7 days before or after the date the patient is scheduled to receive the second initiation injections.

Continuation Injections (CABENUVA 600-mg/900-mg Kit)

After the 2 initiation doses given consecutively 1 month apart (Months 1 and 2), the recommended continuation injection doses (Month 4 onwards) of CABENUVA are a single 600-mg (3-mL) intramuscular injection of cabotegravir and a single 900-mg (3-mL) intramuscular injection of rilpivirine administered every 2 months (Table 2). Administer cabotegravir and rilpivirine at separate gluteal injection sites (on opposite sides or at least 2 cm apart) during the same visit [see Dosage and Administration (2.9)]. Patients may be given CABENUVA up to 7 days before or after the date the patient is scheduled to receive the injections.

Table 2. Recommended Dosing Schedule with Optional Oral Lead-In or Direct to Injection for Every-2-Month Injection
Drug | Optional Oral Lead-Ina; (at Least 28 Days) | Intramuscular (Gluteal) Injectionsb
Drug | Month (at Least 28 Days) Prior to Starting Injections | Initiate Injectionsc at Month 1, Month 2, and then Every 2 Months Onwards (Starting at Month 4)
Cabotegravir | 30 mg once daily with a meal | 600 mg (3 mL)
Rilpivirine | 25 mg once daily with a meal | 900 mg (3 mL)
a The optional oral therapy should be continued until the day the first injection is administered.
b For the every-2-month injection dosing schedule in adults, Initiation Injections are injections administered at Month 1 and Month 2 and Continuation Injections are injections administered every 2 months onwards (starting Month 4).
c Given on the last day of current antiretroviral therapy or oral lead-in if used.

2.6 Dosing Recommendations When Switching from Monthly to Every-2-Month Intramuscular Injections

Patients switching from a monthly continuation injection schedule (a single 400-mg [2-mL] gluteal intramuscular injection of cabotegravir and a single 600-mg [2-mL] intramuscular injection of rilpivirine) to an every-2-month continuation injection dosing schedule should receive a single 600-mg (3-mL) intramuscular injection of cabotegravir and a single 900-mg (3-mL) intramuscular injection of rilpivirine administered 1 month after the last monthly continuation injections and then every 2 months thereafter. Cabotegravir and rilpivirine injections should be administered at separate gluteal injection sites (on opposite sides or at least 2 cm apart) during the same visit [see Dosage and Administration (2.9)].

2.7 Dosing Recommendations When Switching from Every-2-Month to Monthly Intramuscular Injections

Patients switching from an every-2-month continuation injection schedule (a single 600-mg [3-mL] intramuscular injection of cabotegravir and a single 900-mg [3-mL] intramuscular injection of rilpivirine) to a monthly continuation dosing schedule should receive a single 400-mg (2-mL) intramuscular injection of cabotegravir and a single 600-mg (2-mL) intramuscular injection of rilpivirine 2 months after the last every-2‑month continuation injection and then monthly thereafter. Cabotegravir and rilpivirine injections should be administered at separate gluteal injection sites (on opposite sides or at least 2 cm apart) during the same visit [see Dosage and Administration (2.9)].

2.8 Recommended Dosing Schedule for Missed Injections

Adherence to the injection dosing schedule is strongly recommended [see Dosage and Administration (2.2)]. Patients who miss a scheduled injection visit should be clinically reassessed to ensure resumption of therapy remains appropriate. Refer to Table 3 for dosing recommendations after missed injections.

Planned Missed Injections for Patients on the Monthly Dosing Schedule

If a patient plans to miss a scheduled injection visit by more than 7 days, VOCABRIA in combination with EDURANT once daily may be used for up to 2 months to replace missed injection visits, or any other fully suppressive oral antiretroviral regimen may be used until injections are resumed. The recommended oral daily dose is one 30-mg tablet of VOCABRIA (cabotegravir) and one 25-mg tablet of EDURANT (rilpivirine). Take VOCABRIA with EDURANT at approximately the same time each day with a meal.

The first dose of oral therapy should be taken 1 month (+/-7 days) after the last injection dose of CABENUVA and continued until the day injection dosing is restarted. Refer to Table 3 for injection dosing recommendations. For oral therapy with VOCABRIA and EDURANT of durations greater than 2 months, an alternative oral regimen is recommended.

Unplanned Missed Injections for Patients on the Monthly Dosing Schedule

If monthly injections are missed or delayed by more than 7 days and oral therapy has not been taken in the interim, clinically reassess the patient to determine if resumption of injection dosing remains appropriate [see Warnings and Precautions (5.6)]. If injection dosing will be continued, see Table 3 for dosing recommendations.

Table 3. Injection Dosing Recommendations after Missed Injections for Patients on the Monthly Dosing Schedulea
Time since Last Injection | Recommendation
Less than or equal to 2 months | Resume with 400-mg (2-mL) cabotegravir and 600-mg (2-mL) rilpivirine gluteal intramuscular monthly injections as soon as possible.
Greater than 2 months | Re-initiate the patient with 600-mg (3-mL) cabotegravir and 900-mg (3‑mL) rilpivirine gluteal intramuscular injections then continue to follow the 400‑mg (2‑mL) cabotegravir and 600-mg (2-mL) rilpivirine gluteal intramuscular monthly injection dosing schedule.
a Refer to oral dosing recommendations if a patient plans to miss a scheduled injection visit.

Planned Missed Injections for Patients on the Every-2-Month Dosing Schedule

If a patient plans to miss a scheduled injection visit by more than 7 days, VOCABRIA in combination with EDURANT once daily may be used for up to 2 months to replace 1 missed injection visit, or any other fully suppressive oral antiretroviral regimen may be used until injections are resumed. The recommended oral daily dose is one 30‑mg tablet of VOCABRIA (cabotegravir) and one 25‑mg tablet of EDURANT (rilpivirine). Take VOCABRIA with EDURANT at approximately the same time each day with a meal.

The first dose of oral therapy should be taken approximately 2 months after the last injection dose of CABENUVA and continued until the day injection dosing is restarted. Refer to Table 4 for injection dosing recommendations. For oral therapy with VOCABRIA and EDURANT of durations greater than 2 months, an alternative oral regimen is recommended.

Unplanned Missed Injections for Patients on the Every-2-Month Dosing Schedule

If a scheduled every-2-month injection visit is missed or delayed by more than 7 days and oral therapy has not been taken in the interim, clinically reassess the patient to determine if resumption of injection dosing remains appropriate [see Warnings and Precautions (5.6)]. If the every-2‑month dosing schedule will be continued, see Table 4 for dosing recommendations.

Table 4. Injection Dosing Recommendations after Missed Injections for Patients on the Every-2-Month Dosing Schedule
Missed Injection Visit | Time since Last Injection | Recommendation
Injection 2 (Month 2) | Less than or equal to 2 months | Resume with 600-mg (3-mL) cabotegravir and 900‑mg (3‑mL) rilpivirine intramuscular injections as soon as possible, then continue to follow the every-2-month injection dosing schedule.
Injection 2 (Month 2) | Greater than 2 months | Re-initiate the patient with 600-mg (3-mL) cabotegravir and 900-mg (3‑mL) rilpivirine intramuscular injections, followed by the second initiation injection dose 1 month later. Then continue to follow the every-2-month injection dosing schedule thereafter.
Injection 3 or later (Month 4 onwards) | Less than or equal to 3 months | Resume with 600-mg (3-mL) cabotegravir and 900‑mg (3‑mL) rilpivirine intramuscular injections as soon as possible and continue with the every‑2‑month injection dosing schedule.
Injection 3 or later (Month 4 onwards) | Greater than 3 months | Re-initiate the patient with 600-mg (3-mL) cabotegravir and 900-mg (3‑mL) rilpivirine intramuscular injections, followed by the second initiation injection dose 1 month later. Then continue with the every-2-month injection dosing schedule thereafter.

2.9 Administration Instructions for Injections

Refer to the Instructions for Use for complete administration instructions with illustrations. Carefully follow these instructions and ensure that the vial adaptor is used correctly when preparing the suspension for injection to avoid leakage.

A complete dose requires 2 injections: 1 injection of cabotegravir and 1 injection of rilpivirine [see Dosage and Administration (2.4, 2.5)].

Cabotegravir and rilpivirine are suspensions for gluteal intramuscular injection that do not need further dilution or reconstitution.

Administer each injection at separate gluteal injection sites (on opposite sides or at least 2 cm apart) during the same visit. The ventrogluteal site is recommended. A dorsogluteal approach (upper outer quadrant) is acceptable, if preferred by the healthcare professional. Do not administer by any other route or anatomical site. Consider the body mass index (BMI) of the patient to ensure that the needle length is sufficient to reach the gluteus muscle. Longer needle lengths (not included in the dosing kit) may be required for patients with higher BMI (example: >30 kg/m^2) to ensure that injections are administered intramuscularly as opposed to subcutaneously. The administration order of cabotegravir and rilpivirine injections is not important.

Before preparing the injections, remove CABENUVA from the refrigerator and wait at least 15 minutes to allow the medicines to come to room temperature. The vials may remain in the carton at room temperature for up to 6 hours; do not put back into the refrigerator. If not used within 6 hours, the medication must be discarded.

Parenteral drug products should be inspected visually for particulate matter and discoloration prior to administration, whenever solution and container permit. The cabotegravir vial has a brown tint to the glass that may limit visual inspection. Discard CABENUVA if either medicine exhibits particulate matter or discoloration.

Shake each vial of CABENUVA vigorously so that the suspensions look uniform before injecting. Small air bubbles are expected and acceptable.

Once the suspensions have been drawn into the respective syringes, the injections should be administered as soon as possible, but may remain in the syringes for up to 2 hours. The filled syringes should not be placed in the refrigerator. If the medicine remains in the syringes for more than 2 hours, the filled syringes and needles must be discarded [see How Supplied/Storage and Handling (16)].

3 DOSAGE FORMS AND STRENGTHS

Injection:

- Kit of single-dose vials of 400 mg/2 mL (200 mg/mL) of cabotegravir extended-release injectable suspension and 600 mg/2 mL (300 mg/mL) of rilpivirine extended-release injectable suspension. (3)
- Kit of single-dose vials of 600 mg/3 mL (200 mg/mL) of cabotegravir extended-release injectable suspension and 900 mg/3 mL (300 mg/mL) of rilpivirine extended-release injectable suspension. (3)

4 CONTRAINDICATIONS

CABENUVA is contraindicated in patients:

- with previous hypersensitivity reaction to cabotegravir or rilpivirine [see Warnings and Precautions (5.1)].
- receiving the following coadministered drugs for which significant decreases in cabotegravir and/or rilpivirine plasma concentrations may occur due to uridine diphosphate glucuronosyltransferase (UGT)1A1 and/or cytochrome P450 (CYP)3A enzyme induction, which may result in loss of virologic response [see Drug Interactions (7), Clinical Pharmacology (12.3)]:
  - Anticonvulsants: Carbamazepine, oxcarbazepine, phenobarbital, phenytoin
  - Antimycobacterials: Rifabutin, rifampin, rifapentine
  - Glucocorticoid (systemic): Dexamethasone (more than a single-dose treatment)
  - Herbal product: St John’s wort (Hypericum perforatum)

5 WARNINGS AND PRECAUTIONS

5.1 Hypersensitivity Reactions

Serious or severe hypersensitivity reactions have been reported with cabotegravir- and rilpivirine-containing regimens. Reactions associated with cabotegravir include Stevens-Johnson syndrome (SJS)/toxic epidermal necrolysis (TEN) [see Adverse Reactions (6.2)]. Reactions associated with rilpivirine-containing regimens include cases of drug reaction with eosinophilia and systemic symptoms (DRESS) [see Adverse Reactions (6.1, 6.2)]. While some skin reactions were accompanied by constitutional symptoms such as fever, other skin reactions were associated with organ dysfunctions, including elevations in hepatic serum biochemistries. Administration of cabotegravir and rilpivirine oral lead-in dosing was used in clinical studies to help identify patients who may be at risk of a hypersensitivity reaction [see Dosage and Administration (2.3), Contraindications (4)]. Remain vigilant and discontinue CABENUVA if a hypersensitivity reaction is suspected [see Contraindications (4), Adverse Reactions (6)].

Discontinue CABENUVA immediately if signs or symptoms of hypersensitivity reactions develop (including, but not limited to, severe rash, or rash accompanied by fever, general malaise, fatigue, muscle or joint aches, blisters, mucosal involvement [oral blisters or lesions], conjunctivitis, facial edema, hepatitis, eosinophilia, angioedema, difficulty breathing). Clinical status, including liver transaminases, should be monitored and appropriate therapy initiated. For information regarding the long-acting properties of CABENUVA, [see Warnings and Precautions (5.6)]. Administer oral lead-in dosing prior to administration of CABENUVA to help identify patients who may be at risk of a hypersensitivity reaction [see Dosage and Administration (2.3), Contraindications (4)].

5.2 Post-Injection Reactions

In clinical trials, serious post-injection reactions were reported within minutes after the injection of rilpivirine. These events included symptoms such as dyspnea, bronchospasm, agitation, abdominal cramping, rash/urticaria, dizziness, flushing, sweating, oral numbness, changes in blood pressure, and pain (e.g., back and chest). These events were reported in <1% of participants and began to resolve within minutes after the injection, with some patients receiving supportive care. These events may have been associated with accidental intravenous administration during the intramuscular injection procedure [see Adverse Reactions (6.1)].

Carefully follow the Instructions for Use when preparing and administering CABENUVA. The suspensions should be injected slowly via intramuscular injection, and care should be taken to avoid accidental intravenous administration [see Dosage and Administration (2.9)]. Observe patients briefly (approximately 10 minutes) after the injection. If a patient experiences a post-injection reaction, monitor and treat as clinically indicated.

5.3 Hepatotoxicity

Hepatotoxicity has been reported in patients receiving cabotegravir or rilpivirine with or without known pre-existing hepatic disease or identifiable risk factors [see Adverse Reactions (6.1)].

Patients with underlying liver disease or marked elevations in transaminases prior to treatment may be at increased risk for worsening or development of transaminase elevations.

Monitoring of liver chemistries is recommended and treatment with CABENUVA should be discontinued if hepatotoxicity is suspected. For information regarding the long-acting properties of CABENUVA, [see Warnings and Precautions (5.6)].

5.4 Depressive Disorders

Depressive disorders (including depressed mood, depression, major depression, mood altered, mood swings, dysphoria, negative thoughts, suicidal ideation, suicide attempt) have been reported with CABENUVA or the individual drug products [see Adverse Reactions (6.1)]. Promptly evaluate patients with depressive symptoms to assess whether the symptoms are related to CABENUVA and to determine whether the risks of continued therapy outweigh the benefits.

5.5 Risk of Adverse Reactions or Loss of Virologic Response Due to Drug Interactions

The concomitant use of CABENUVA and other drugs may result in known or potentially significant drug interactions, some of which may lead to adverse events, loss of virologic response of CABENUVA, and possible development of viral resistance [see Contraindications (4), Drug Interactions (7.4)].

Rilpivirine 75-mg and 300-mg once-daily oral doses (3 and 12 times, respectively, the recommended oral dosage) in healthy adults prolonged the QTc interval with mean steady-state Cmax values 4.4- and 11.6-fold, respectively, higher than Cmax values associated with the recommended 600-mg monthly dose of rilpivirine extended-release injectable suspension and 4.1- and 10.7-fold, respectively, higher than Cmax values associated with the recommended 900-mg every-2-month dose of rilpivirine extended‑release injectable suspension [see Clinical Pharmacology (12.2)]. CABENUVA should be used with caution in combination with drugs with a known risk of Torsade de Pointes [see Drug Interactions (7.3, 7.4)].

See Table 8 for steps to prevent or manage these possible and known significant drug interactions, including dosing recommendations. Consider the potential for drug interactions prior to and during therapy with, and after discontinuation of, CABENUVA; review concomitant medications during therapy with CABENUVA [see Drug Interactions (7.4)].

5.6 Long-Acting Properties and Potential Associated Risks with CABENUVA

Residual concentrations of both cabotegravir and rilpivirine may remain in the systemic circulation of patients for prolonged periods (up to 12 months or longer). It is important to carefully select patients who agree to the required monthly or every-2-month injection dosing schedule because non-adherence to monthly or every-2-month injections or missed doses could lead to loss of virologic response and development of resistance [see Dosage and Administration (2.2), Adverse Reactions (6.1), Drug Interactions (7.4)].

To minimize the potential risk of developing viral resistance, it is essential to initiate an alternative, fully suppressive antiretroviral regimen no later than 1 month after the final injections of CABENUVA when dosed monthly and no later than 2 months after the final injections of CABENUVA when dosed every 2 months. If virologic failure is suspected, switch the patient to an alternative regimen as soon as possible.

6 ADVERSE REACTIONS

The following adverse reactions are described below and in other sections of the labeling:

- Hypersensitivity reactions [see Warnings and Precautions (5.1)]
- Post-injection reactions [see Warnings and Precautions (5.2)]
- Hepatotoxicity [see Warnings and Precautions (5.3)]
- Depressive disorders [see Warnings and Precautions (5.4)]

6.1 Clinical Trials Experience

Because clinical trials are conducted under widely varying conditions, adverse reaction rates observed in the clinical trials of a drug cannot be directly compared with rates in the clinical trials of another drug and may not reflect rates observed in practice.

Clinical Trials Experience in Adults

The safety assessment of CABENUVA is based on the analysis of pooled 48-week data from 1,182 virologically suppressed participants with HIV-1 infection in 2 international, multicenter, open-label pivotal trials, FLAIR and ATLAS, and 1,045 virologically suppressed participants from the ATLAS-2M trial [see Clinical Studies (14.1)]. Additional safety information from other ongoing or earlier clinical trials in the cabotegravir and rilpivirine program have been considered in assessing the overall safety profile of CABENUVA.

Adverse reactions were reported following exposure to CABENUVA extended-release injectable suspensions (median time exposure at the time of analysis: 54 weeks in FLAIR and ATLAS, and 64 weeks in ATLAS-2M) and data from VOCABRIA (cabotegravir) tablets and EDURANT (rilpivirine) tablets administered in combination as oral lead-in therapy (median time exposure: 5.3 weeks in FLAIR and ATLAS, and 5.6 weeks in ATLAS-2M). Adverse reactions included those attributable to both the oral and injectable formulations of cabotegravir and rilpivirine administered as a combination regimen. Refer to the prescribing information for EDURANT (rilpivirine) for other adverse reactions associated with oral rilpivirine.

The most common adverse reactions regardless of severity reported in ≥2% of adult participants from FLAIR and ATLAS at Week 48 are presented in Table 5. Selected laboratory abnormalities are included in Table 7. At Week 96, the overall safety profile for FLAIR was consistent with that observed at Week 48, with no new safety findings identified.

In the extension phase of the FLAIR study at Week 124, the overall safety profile was consistent with that observed at Week 48 and when injection therapy with CABENUVA was initiated directly without the oral lead-in phase.

Overall, 4% of participants in the group receiving CABENUVA and 2% of participants in the control group in FLAIR and ATLAS discontinued due to adverse events. Non-injection-site-related adverse events leading to discontinuation and occurring in more than 1 participant were headache, diarrhea, hepatitis A, and acute hepatitis B (all with an incidence <1%). In ATLAS-2M, 2% of participants in both treatment groups discontinued due to adverse events. Non-injection-site–related adverse events leading to discontinuation and occurring in more than 1 participant in ATLAS-2M were fatigue, pyrexia, headache, presyncope, acute hepatitis B, hyperhidrosis, and abnormal dreams that occurred with an incidence of ≤1% in either treatment group.

Table 5. Adverse Reactionsa (Grades 1 to 4) Reported in at Least 2% of Participants with HIV-1 Infection in FLAIR and ATLAS Trials (Week 48 Pooled Analyses)
Adverse Reactions | Cabotegravir plus Rilpivirine; Once Monthly; (n = 591) |  | Current Antiretroviral Regimen; (n = 591)
Adverse Reactions | All Grades | At Least Grade 2 | All Grades | At Least Grade 2
Injection site reactionsb | 83% | 37% | 0 | 0
Pyrexiac | 8% | 2% | 0 | 0
Fatigued | 5% | 1% | <1% | <1%
Headache | 4% | <1% | <1% | <1%
Musculoskeletal paine | 3% | 1% | <1% | 0
Nausea | 3% | <1% | 1% | <1%
Sleep disordersf | 2% | <1% | <1% | 0
Dizziness | 2% | <1% | <1% | 0
Rashg | 2% | <1% | 0 | 0
a Adverse reactions defined as “treatment-related” as assessed by the investigator.
b See Injection-Associated Adverse Reactions for additional information.
c Pyrexia: includes pyrexia, feeling hot, chills, influenza-like illness, body temperature increased.
d Fatigue: includes fatigue, malaise, asthenia.
e Musculoskeletal pain: includes musculoskeletal pain, musculoskeletal discomfort, back pain, myalgia, pain in extremity.
f Sleep disorders: includes insomnia, poor quality sleep, somnolence.
g Rash: includes erythema, pruritus, pruritus generalized, purpura, rash, rash- erythematous, generalized, macular.

In ATLAS-2M, the type and frequency of adverse reactions reported in participants receiving CABENUVA once monthly or CABENUVA once every 2 months for 48 weeks were similar. Differences between treatment arms were reported for the types of injection-associated adverse reactions (see Injection-Associated Adverse Reactions for additional information).

Injection-Associated Adverse Reactions: Local Injection Site Reactions (ISRs): In the 3 Phase 3 studies, FLAIR, ATLAS, and ATLAS‑2M, the most frequent adverse reactions associated with the intramuscular administration of CABENUVA were ISRs.

In the pooled analysis of FLAIR and ATLAS, 83% of participants reported any injection site reaction with the monthly dosing regimen, with 1% of participants who discontinued treatment with CABENUVA because of ISRs. After 14,682 injections, 3,663 ISRs were reported. The severity of ISRs was generally mild (Grade 1: 75% of participants) or moderate (Grade 2: 36% of participants). Four percent (4%) of participants experienced severe (Grade 3) ISRs, and no participant experienced Grade 4 ISRs. The median duration of overall ISR events was 3 days. The most commonly reported ISR in FLAIR and ATLAS was pain/discomfort, with 79% reported in the group receiving CABENUVA.

In ATLAS-2M, 75% of participants reported any injection site reaction in both the monthly and every‑2‑month dosing regimens, with <1% of participants who discontinued treatment with CABENUVA because of ISRs. When dosing monthly, after 15,711 injections, 3,152 ISRs were reported. When dosing every 2 months, after 8,470 injections, 2,507 ISRs were reported. The severity of ISRs was generally mild (Grade 1: 70% and 71% of participants) or moderate (Grade 2: 28% and 27% of participants) in monthly and every‑2‑month dosing regimens, respectively. Four percent (4%) of participants in the monthly group and 3% of participants in the every‑2‑month group experienced severe (Grade 3) ISRs, and no participant experienced Grade 4 ISRs. The median duration of overall ISR events was 3 days for both dosing regimens. The most commonly reported ISR in ATLAS‑2M was pain/discomfort, with 71% and 73% reported in the monthly and every‑2‑month dosing regimens, respectively. The severity and duration of ISRs, including pain/discomfort, were similar for both dosing regimens and in participants without prior exposure to CABENUVA.

The most commonly reported ISR (Grades 1 to 3) in at least 1% of adult participants in the pooled analyses from FLAIR and ATLAS, and from ATLAS‑2M, are presented in Table 6. The side‑by‑side tabulation is to simplify presentation; direct comparison across trials should not be made due to differing trials.

Table 6. Injection Site Reactions (Grades 1 to 3) Reported in at Least 1% of Participants in FLAIR and ATLAS (Pooled Analysis) and ATLAS-2M Trials (Week 48 Analysis)
Injection Site Reactions | FLAIR and ATLAS | ATLAS-2M
Injection Site Reactions | Cabotegravir plus Rilpivirine; Once Monthly; (n = 591) | Cabotegravir plus Rilpivirine; Once Every 2 Months; (n = 522) | Cabotegravir plus Rilpivirine; Once Monthly; (n = 523)
Any injection site reaction | 83% | 75% | 75%
Pain/discomfort | 79% | 73% | 71%
Nodules | 14% | 10% | 17%
Induration | 12% | 8% | 7%
Swelling | 8% | 6% | 5%
Erythema | 4% | 2% | 3%
Pruritus | 4% | 5% | 5%
Bruising/discoloration | 3% | 2% | 2%
Warmth | 2% | 1% | 2%
Hematoma | 2% | <1% | 3%
Anesthesia, abscess, cellulitis, and hemorrhage at the injection site were each reported in <1% of participants.

Other Injection-Associated Adverse Reactions: In the ATLAS and FLAIR clinical trials, an increased incidence of pyrexia (8%) was reported by participants receiving cabotegravir plus rilpivirine injections compared with no events among participants receiving current antiretroviral regimen. In ATLAS and FLAIR, no cases were serious or led to withdrawal and the occurrences of pyrexia may represent a response to administration of CABENUVA via intramuscular injection. In ATLAS-2M, 1 participant in each arm reported pyrexia that led to withdrawal.

In ATLAS and FLAIR, reports of musculoskeletal pain (3%) and less frequently, sciatica, were also more common in participants receiving cabotegravir plus rilpivirine compared with the current antiretroviral regimen and some events had a temporal association with injection.

Vasovagal or pre-syncopal reactions were reported in <1% of participants after injection with rilpivirine or cabotegravir.

Less Common Adverse Reactions: The following select adverse reactions (regardless of severity) occurred in <2% of participants receiving cabotegravir plus rilpivirine.

Gastrointestinal Disorders: Abdominal pain (including upper abdominal pain), gastritis, dyspepsia, vomiting, diarrhea, and flatulence.

Hepatobiliary Disorders: Hepatotoxicity.

Investigations: Weight increase (see below).

Psychiatric Disorders: Anxiety (including anxiety and irritability), depression, abnormal dreams, suicidal ideation, and suicide attempt (these events were observed primarily in participants with a pre-existing history of depression or other psychiatric illness).

Skin and Hypersensitivity Reactions: Hypersensitivity reactions.

Weight Increase: At Week 48, participants in FLAIR and ATLAS who received cabotegravir plus rilpivirine had a median weight gain of 1.5 kg; those in the current antiretroviral regimen group had a median weight gain of 1.0 kg (pooled analysis). In the FLAIR trial, the median weight gain in participants receiving cabotegravir plus rilpivirine or a dolutegravir-containing regimen was 1.3 kg and 1.5 kg, respectively, compared with 1.8 kg and 0.3 kg, respectively, in the ATLAS trial in participants receiving either cabotegravir plus rilpivirine or a protease inhibitor-, non-nucleoside reverse transcriptase inhibitor (NNRTI)-, or integrase strand transfer inhibitor (INSTI)-containing regimen, respectively. At Week 48, participants in ATLAS-2M who received cabotegravir plus rilpivirine in both the monthly and every-2-month treatment arms had a median weight gain of 1.0 kg.

Laboratory Abnormalities: Selected laboratory abnormalities with a worsening grade from baseline and representing the worst-grade toxicity are presented in Table 7. The side-by-side tabulation is to simplify presentation; direct comparison across trials should not be made due to differing trials.

Table 7. Selected Laboratory Abnormalities (Grades 3 to 4, Week 48) in FLAIR and ATLAS (Pooled Analyses) and ATLAS-2M Trials
Laboratory Parameter | FLAIR and ATLAS |  | ATLAS-2M
Laboratory Parameter | Cabotegravir plus Rilpivirine Once Monthly; (n = 591) | Current Antiretroviral Regimen; (n = 591) | Cabotegravir plus Rilpivirine Once Every 2 Months; (n = 522) | Cabotegravir plus Rilpivirine Once Monthly; (n = 523)
ALT (≥5.0 x ULN) | 2% | <1% | <1% | <1%
AST (≥5.0 x ULN) | 2% | <1% | <1% | 1%
Total bilirubin (≥2.6 x ULN) | <1% | <1% | <1% | <1%
Creatine phosphokinase (≥10.0 x ULN) | 8% | 4% | 3% | 4%
Lipase (≥3.0 x ULN) | 5% | 3% | 3% | 2%
ALT = Alanine Aminotransferase, ULN = Upper limit of normal, AST = Aspartate Transaminase.

Changes in Total Bilirubin: Small, non-progressive increases in total bilirubin (without clinical jaundice) were observed with cabotegravir plus rilpivirine. These changes are not considered clinically relevant as they likely reflect competition between cabotegravir and unconjugated bilirubin for a common clearance pathway (UGT1A1) [see Clinical Pharmacology (12.3)].

Serum Cortisol: In pooled Phase 3 trials of EDURANT (rilpivirine), the overall mean change from baseline in basal cortisol was -0.69 (-1.12, 0.27) mcg/dL in the group receiving EDURANT compared with -0.02 (-0.48, 0.44) mcg/dL in the control group. Abnormal responses to ACTH stimulation tests were also higher in the group receiving EDURANT. The clinical significance of the higher abnormal rate of ACTH stimulation tests in the group receiving EDURANT is not known. Refer to the prescribing information for EDURANT for additional information.

Clinical Trial Experience in Adolescents

Based on data from the Week 16 (cohort 1) and Week 24 (cohort 2) analyses of the MOCHA study, the safety profile in adolescents (aged 12 to younger than 18 years and weighing ≥35 kg) was consistent with the safety profile established with cabotegravir plus rilpivirine in adults [see Clinical Studies (14.2)].

In cohort 1, 55 virologically suppressed adolescents with HIV-1 received background antiretroviral therapy in addition to either oral cabotegravir (n = 30) followed by injectable cabotegravir (n = 29), or oral rilpivirine (n = 25) followed by injectable rilpivirine (n = 23). Adverse reactions were reported in 38% of adolescents receiving either cabotegravir or rilpivirine. Thirty-three percent of participants reported at least 1 ISR. All ISRs were Grade 1 or Grade 2. Two participants had Grade 3 adverse reactions of hypersensitivity (n = 1, oral rilpivirine) and insomnia (n = 1, injectable cabotegravir). The Grade 3 adverse reaction of drug hypersensitivity led to discontinuation of rilpivirine during oral lead-in. The adverse reactions reported by more than one participant (regardless of severity) were injection site pain (n = 18), headache (n = 2), hypersensitivity (n = 2), insomnia (n = 2), and nausea (n = 2).

In cohort 2, 144 virologically suppressed adolescents with HIV-1 received oral cabotegravir plus oral rilpivirine followed by injectable cabotegravir plus injectable rilpivirine. Adverse reactions were reported in 35% of adolescents receiving cabotegravir plus rilpivirine. Thirty-four percent of participants reported at least 1 ISR. The majority of these participants experienced Grade 1 or Grade 2 ISRs. Two participants had Grade 3 ISRs consisting of injection site abscess (n = 2) and injection site pain in one of these two participants (symptoms resolved in both participants). All non-ISR adverse reactions were ≤ Grade 2. Non-injection-site associated adverse reactions reported by more than one participant (regardless of severity) were headache (n = 3), nausea (n = 2), rash (n = 2) and rash pruritic (n = 2).

6.2 Postmarketing Experience

The following adverse reactions have been identified during postmarketing experience in patients receiving cabotegravir- or oral-rilpivirine-containing regimens. Because these reactions are reported voluntarily from a population of uncertain size, it is not always possible to reliably estimate their frequency or establish a causal relationship to drug exposure.

Immune System Disorders

Hypersensitivity reactions (including angioedema and urticaria) [see Warnings and Precautions (5.1)].

Renal and Genitourinary Disorders

Nephrotic syndrome.

Skin and Subcutaneous Tissue Disorders

Severe skin and hypersensitivity reactions, including DRESS, Stevens-Johnson syndrome (SJS)/toxic epidermal necrolysis (TEN) [see Warnings and Precautions (5.1)].

7 DRUG INTERACTIONS

7.1 Concomitant Use with Other Antiretroviral Medicines

Because CABENUVA is a complete regimen, coadministration with other antiretroviral medications for the treatment of HIV-1 infection is not recommended [see Indications and Usage (1)].

7.2 Use of Other Antiretroviral Drugs after Discontinuation of CABENUVA

Residual concentrations of cabotegravir and rilpivirine may remain in the systemic circulation of patients for prolonged periods (up to 12 months or longer). These residual concentrations are not expected to affect the exposures of antiretroviral drugs that are initiated after discontinuation of CABENUVA [see Warnings and Precautions (5.6), Drug Interactions (7.4), Clinical Pharmacology (12.3)].

7.3 Potential for Other Drugs to Affect CABENUVA

Refer to the prescribing information for VOCABRIA (cabotegravir) and EDURANT (rilpivirine) for additional drug interaction information related to oral cabotegravir and oral rilpivirine, respectively.

Cabotegravir

Cabotegravir is primarily metabolized by UGT1A1 with some contribution from UGT1A9. Drugs that are strong inducers of UGT1A1 or UGT1A9 are expected to decrease cabotegravir plasma concentrations and may result in loss of virologic response; therefore, coadministration of CABENUVA with these drugs is contraindicated [see Contraindications (4)].

Rilpivirine

Rilpivirine is primarily metabolized by CYP3A. Coadministration of CABENUVA and drugs that induce CYP3A may result in decreased plasma concentrations of rilpivirine and loss of virologic response and possible resistance to rilpivirine or to the class of NNRTIs [see Contraindications (4), Drug Interactions (7.4)]. Coadministration of CABENUVA and drugs that inhibit CYP3A may result in increased plasma concentrations of rilpivirine [see Drug Interactions (7.4), Clinical Pharmacology (12.3)].

QT-Prolonging Drugs: At mean steady-state Cmax values 4.4- and 11.6-fold higher than those with the recommended 600‑mg dose of rilpivirine extended-release injectable suspension, rilpivirine may prolong the QTc interval [see Clinical Pharmacology (12.2)]. CABENUVA should be used with caution in combination with drugs with a known risk of Torsade de Pointes [see Warnings and Precautions (5.5), Drug Interactions (7.4)].

7.4 Established and Other Potentially Significant Drug Interactions

Refer to the prescribing information for VOCABRIA (cabotegravir) and EDURANT (rilpivirine) for additional drug interaction information related to oral cabotegravir and oral rilpivirine, respectively.

Information regarding potential drug interactions with cabotegravir and rilpivirine is provided in Table 8. These recommendations are based on either drug interaction trials following oral administration of cabotegravir or rilpivirine or predicted interactions due to the expected magnitude of the interaction and potential for loss of virologic response [see Contraindications (4), Warnings and Precautions (5.5), Clinical Pharmacology (12.3)]. Table 8 includes potentially significant interactions but is not all inclusive.

Table 8. Drug Interactions with CABENUVA
Concomitant Drug Class:; Drug Name | Effect on Concentration | Clinical Comment
Anticonvulsants:; Carbamazepine; Oxcarbazepine; Phenobarbital; Phenytoin | ↓Cabotegravir; ↓Rilpivirine | Coadministration is contraindicated with CABENUVA due to potential for loss of virologic response and development of resistance [see Contraindications (4)].
Antimycobacterials:; Rifampina; Rifapentine | ↓Cabotegravir; ↓Rilpivirine | Coadministration is contraindicated with CABENUVA due to potential for loss of virologic response and development of resistance [see Contraindications (4)].
Antimycobacterial:; Rifabutina | ↓Cabotegravir; ↔Rifabutin; ↓Rilpivirine | Coadministration is contraindicated with CABENUVA due to potential for loss of virologic response and development of resistance [see Contraindications (4)].
Glucocorticoid (systemic):; Dexamethasone; (more than a single-dose treatment) | ↓Rilpivirine | Coadministration is contraindicated with CABENUVA due to potential for loss of virologic response and development of resistance [see Contraindications (4)].
Herbal product:; St John’s wort (Hypericum perforatum) | ↓Rilpivirine | Coadministration is contraindicated with CABENUVA due to potential for loss of virologic response and development of resistance [see Contraindications (4)].
Macrolide or ketolide antibiotics:; Azithromycin; Clarithromycin; Erythromycin | ↔Cabotegravir; ↑Rilpivirine | Macrolides are expected to increase concentrations of rilpivirine and are associated with a risk of Torsade de Pointes [see Warnings and Precautions (5.5)]. Where possible, consider alternatives, such as azithromycin, which increases rilpivirine concentrations less than other macrolides.
Narcotic analgesic:; Methadonea | ↔Cabotegravir; ↓Methadone; ↔Rilpivirine | No dose adjustment of methadone is required when starting coadministration of methadone with CABENUVA. However, clinical monitoring is recommended as methadone maintenance therapy may need to be adjusted in some patients.
↑ = Increase, ↓ = Decrease, ↔ = No change.
a See Clinical Pharmacology (12.3) for magnitude of interaction.

7.5 Drugs without Clinically Significant Interactions

Cabotegravir

Based on drug interaction study results, the following drugs can be coadministered with cabotegravir (non-antiretrovirals and rilpivirine) or given after discontinuation of cabotegravir (antiretrovirals and non-antiretrovirals) without a dose adjustment: etravirine, midazolam, oral contraceptives containing levonorgestrel and ethinyl estradiol, and rilpivirine [see Clinical Pharmacology (12.3)].

Rilpivirine

Based on drug interaction study results, the following drugs can be coadministered with rilpivirine (non-antiretrovirals and cabotegravir) or given after discontinuation of rilpivirine (antiretrovirals and non-antiretrovirals): acetaminophen, atorvastatin, cabotegravir, chlorzoxazone, dolutegravir, ethinyl estradiol, norethindrone, raltegravir, ritonavir-boosted atazanavir, ritonavir-boosted darunavir, sildenafil, tenofovir alafenamide, and tenofovir disoproxil fumarate [see Clinical Pharmacology (12.3)]. Rilpivirine did not have a clinically significant effect on the pharmacokinetics of digoxin or metformin.

8 USE IN SPECIFIC POPULATIONS

8.1 Pregnancy

Pregnancy Exposure Registry

There is a pregnancy exposure registry that monitors pregnancy outcomes in individuals exposed to CABENUVA during pregnancy. Healthcare providers are encouraged to register patients by calling the Antiretroviral Pregnancy Registry (APR) at 1-800-258-4263.

Risk Summary

There are insufficient human data on the use of CABENUVA during pregnancy to adequately assess a drug-associated risk of birth defects and miscarriage. Discuss the benefit-risk of using CABENUVA with individuals of childbearing potential or during pregnancy.

Cabotegravir and rilpivirine are detected in systemic circulation for up to 12 months or longer after discontinuing injections of CABENUVA; therefore, consideration should be given to the potential for fetal exposure during pregnancy [see Warnings and Precautions (5.6), Drug Interactions (7.2)].

Cabotegravir use in pregnant individuals has not been evaluated. Available data from the APR show no difference in the overall risk of birth defects for rilpivirine compared with the background rate for major birth defects of 2.7% in a United States (U.S.) reference population of the Metropolitan Atlanta Congenital Defects Program (MACDP) (see Data).

The rate of miscarriage is not reported in the APR. The background risk for major birth defects and miscarriage for the indicated population is unknown. The background rate for major birth defects in a U.S. reference population of the MACDP is 2.7%. The estimated background rate of miscarriage in clinically recognized pregnancies in the U.S. general population is 15% to 20%. The APR uses the MACDP as the U.S. reference population for birth defects in the general population. The MACDP evaluates mothers and infants from a limited geographic area and does not include outcomes for births that occurred at <20 weeks’ gestation.

In animal reproduction studies with oral cabotegravir, a delay in the onset of parturition and increased stillbirths and neonatal deaths were observed in a rat pre- and postnatal development study at >28 times the exposure at the recommended human dose (RHD). No evidence of adverse developmental outcomes was observed with oral cabotegravir in rats or rabbits (>28 times or similar to the exposure at the RHD, respectively) given during organogenesis (see Data).

No adverse developmental outcomes were observed when rilpivirine was administered orally at exposures 15 (rats) and 70 (rabbits) times the exposure in humans at the RHD (see Data).

Clinical Considerations

Lower exposures with oral rilpivirine were observed during pregnancy. Viral load should be monitored closely if the patient remains on CABENUVA during pregnancy. Cabotegravir and rilpivirine are detected in systemic circulation for up to 12 months or longer after discontinuing injections of CABENUVA; therefore, consideration should be given to the potential for fetal exposure during pregnancy [see Warnings and Precautions (5.6), Drug Interactions (7.2)].

Data

Human Data:

Rilpivirine: Based on prospective reports to the APR of over 580 exposures to oral rilpivirine-containing regimens during the first trimester of pregnancy and over 200 during second/third trimester of pregnancy, the prevalence of birth defects in live births was 1.5% (95% CI: 0.7% to 2.9%) and 1.5% (95% CI: 0.3% to 4.2%) following first and second/third trimester exposures, respectively, compared with the background birth defect rate of 2.7% in the U.S. reference population of the MACDP. In a clinical trial, total oral rilpivirine exposures were generally lower during pregnancy compared with the postpartum period. Refer to the prescribing information for EDURANT (rilpivirine) for additional information on rilpivirine.

Animal Data: Cabotegravir: Cabotegravir was administered orally to pregnant rats at 0, 0.5, 5, or 1,000 mg/kg/day from 15 days before cohabitation, during cohabitation, and from Gestation Days 0 to 17. There were no effects on fetal viability when fetuses were delivered by caesarean, although a minor decrease in fetal body weight was observed at 1,000 mg/kg/day (>28 times the exposure in humans at the RHD). No drug-related fetal toxicities were observed at 5 mg/kg/day (approximately 13 times the exposure in humans at the RHD), and no drug-related fetal malformations were observed at any dose.

Cabotegravir was administered orally to pregnant rabbits at 0, 30, 500, or 2,000 mg/kg/day from Gestation Days 7 to 19. No drug-related fetal toxicities were observed at 2,000 mg/kg/day (approximately 0.7 times the exposure in humans at the RHD).

In a rat pre- and postnatal development study, cabotegravir was administered orally to pregnant rats at 0, 0.5, 5, or 1,000 mg/kg/day from Gestation Day 6 to Lactation Day 21. A delay in the onset of parturition and increases in the number of stillbirths and neonatal deaths by Lactation Day 4 were observed at 1,000 mg/kg/day (>28 times the exposure in humans at the RHD); there were no alterations to growth and development of surviving offspring. In a cross-fostering study, similar incidences of stillbirths and early postnatal deaths were observed when rat pups born to cabotegravir-treated mothers were nursed from birth by control mothers. There was no effect on neonatal survival of control pups nursed from birth by cabotegravir-treated mothers. A lower dose of 5 mg/kg/day (13 times the exposure at the RHD) was not associated with delayed parturition or neonatal mortality in rats. Studies in pregnant rats showed that cabotegravir crosses the placenta and can be detected in fetal tissue.

Rilpivirine: Rilpivirine was administered orally to pregnant rats (40, 120, or 400 mg/kg/day) and rabbits (5, 10, or 20 mg/kg/day) through organogenesis (on Gestation Days 6 through 17 and 6 through 19, respectively). No significant toxicological effects were observed in embryo-fetal toxicity studies performed with rilpivirine in rats and rabbits at exposures 15 (rats) and 70 (rabbits) times the exposure in humans at the RHD. In a pre- and postnatal development study, rilpivirine was administered orally up to 400 mg/kg/day through lactation. No adverse effects were noted in the offspring at maternal exposures up to 63 times the exposure in humans at the RHD.

8.2 Lactation

Risk Summary

Based on limited data after oral administration, rilpivirine is present in human breast milk. The data do not allow determination of the amount of rilpivirine that is transferred to milk. There are no data on the presence of cabotegravir in human milk. Cabotegravir is present in animal milk (see Data). When a drug is present in animal milk, it is likely that the drug will be present in human milk. It is not known if the components of CABENUVA affect human milk production or have effects on the breastfed infant. Residual exposures in human milk of cabotegravir (if present) and rilpivirine may remain for 12 months or longer after the last injections have been administered [see Warnings and Precautions (5.6)].

Potential risks of breastfeeding include: (1) HIV‑1 transmission (in HIV-1–negative infants), (2) developing viral resistance (in HIV-1–positive infants), and (3) adverse reactions in a breastfed infant similar to those seen in adults.

Data

Cabotegravir: Animal lactation studies with cabotegravir have not been conducted. However, cabotegravir was detected in the plasma of nursing pups on Lactation Day 10 in the rat pre- and postnatal development study.

8.4 Pediatric Use

The safety and effectiveness of CABENUVA have been established in adolescents aged 12 to younger than 18 years and weighing at least 35 kg, which is supported by the following:

- Trials in adults [see Clinical Studies (14.1)]
- MOCHA (NCT03497676) trial in adolescents, in which virologically suppressed adolescents with HIV-1 (aged 12 to younger than 18 years and weighing at least 35 kg) received either cabotegravir or rilpivirine in addition to their background antiretroviral regimen (cohort 1), or cabotegravir plus rilpivirine as a complete regimen (cohort 2) [see Adverse Reactions (6.1), Clinical Pharmacology (12.3), Clinical Studies (14.2)].

The safety and efficacy in adolescents (aged 12 to younger than 18 years and weighing at least 35 kg) were similar to that in adults and there was no clinically significant change in exposure for the components of CABENUVA [see Adverse Reactions (6.1)]. The efficacy of CABENUVA in adolescents is extrapolated from adults with support from pharmacokinetic analyses showing similar drug exposure and additional supportive efficacy data from the MOCHA study [see Clinical Pharmacology (12.3), Clinical Studies (14.2)].

The safety, efficacy, and pharmacokinetics of CABENUVA have not been established in pediatric patients younger than 12 years of age or weighing <35 kg.

8.5 Geriatric Use

Clinical trials of CABENUVA did not include sufficient numbers of participants aged 65 years and older to determine whether they respond differently from younger participants. In general, caution should be exercised in administration of CABENUVA in elderly patients, reflecting greater frequency of decreased hepatic, renal, or cardiac function and of concomitant disease or other drug therapy [see Clinical Pharmacology (12.3)].

8.6 Renal Impairment

Based on studies with oral cabotegravir and population pharmacokinetic analyses of oral rilpivirine, no dosage adjustment of CABENUVA is necessary for patients with mild (creatinine clearance ≥60 to <90 mL/min) or moderate renal impairment (creatinine clearance ≥30 to <60 mL/min). In patients with severe renal impairment (creatinine clearance 15 to <30 mL/min) or end-stage renal disease (creatinine clearance <15 mL/min), increased monitoring for adverse effects is recommended [see Clinical Pharmacology (12.3)]. In patients with end-stage renal disease not on dialysis, effects on the pharmacokinetics of cabotegravir or rilpivirine are unknown. As cabotegravir and rilpivirine are >99% protein bound, dialysis is not expected to alter exposures of cabotegravir or rilpivirine.

8.7 Hepatic Impairment

Based on separate studies with oral cabotegravir and oral rilpivirine, no dosage adjustment of CABENUVA is necessary for patients with mild or moderate hepatic impairment (Child-Pugh A or B). The effect of severe hepatic impairment (Child-Pugh C) on the pharmacokinetics of cabotegravir or rilpivirine is unknown [see Clinical Pharmacology (12.3)].

10 OVERDOSAGE

There is no known specific treatment for overdose with cabotegravir or rilpivirine. If overdose occurs, monitor the patient and apply standard supportive treatment as required, including monitoring of vital signs and ECG (QT interval) as well as observation of the clinical status of the patient. As both cabotegravir and rilpivirine are highly bound to plasma proteins, it is unlikely that either would be significantly removed by dialysis. Consider the prolonged exposure to cabotegravir and rilpivirine (components of CABENUVA) following an injection when assessing treatment needs and recovery [see Warnings and Precautions (5.6)].

11 DESCRIPTION

CABENUVA contains cabotegravir extended-release injectable suspension, an HIV INSTI, co-packaged with rilpivirine extended-release injectable suspension, an HIV NNRTI.

Cabotegravir

The chemical name for cabotegravir is (3S,11aR)-N-[(2,4-difluorophenyl)methyl]-6-hydroxy-3-methyl-5,7-dioxo-2,3,5,7,11,11a-hexahydro[1,3]oxazolo[3,2-a]pyrido[1,2-d]pyrazine-8-carboxamide. The empirical formula is C19H17F2N3O5 and the molecular weight is 405.35 g/mol. It has the following structural formula:

Cabotegravir extended-release injectable suspension is a white to light pink free-flowing suspension for intramuscular injection in a sterile single-dose vial. Each vial contains 2 mL or 3 mL of the following: cabotegravir 200 mg/mL and the inactive ingredients mannitol (35 mg/mL), polyethylene glycol (PEG) 3350 (20 mg/mL), polysorbate 20 (20 mg/mL), and Water for Injection.

The vial stoppers are not made with natural rubber latex.

Rilpivirine

The chemical name for rilpivirine is 4-[[4-[[4-[(E)-2-cyanoethenyl]-2,6-dimethylphenyl]amino]-2-pyrimidinyl]amino]benzonitrile. Its molecular formula is C22H18N6 and its molecular weight is 366.42. Rilpivirine has the following structural formula:

Rilpivirine extended-release injectable suspension is a white to off-white suspension for intramuscular injection. Each sterile single-dose vial contains 2 mL or 3 mL of the following: rilpivirine 300 mg/mL and the following inactive ingredients: citric acid monohydrate (1 mg/mL), dextrose to ensure isotonicity, monobasic sodium phosphate (1.74 mg/mL), poloxamer 338 (50 mg/mL), sodium hydroxide to adjust pH, and Water for Injection.

The vial stoppers are not made with natural rubber latex.

12 CLINICAL PHARMACOLOGY

12.1 Mechanism of Action

CABENUVA contains 2 long-acting HIV-1 antiretroviral drugs, cabotegravir and rilpivirine [see Microbiology (12.4)].

12.2 Pharmacodynamics

Cardiac Electrophysiology

At a dose of cabotegravir 150 mg orally every 12 hours (10 times the recommended total daily oral lead-in dosage of CABENUVA), the QT interval is not prolonged to any clinically relevant extent. Administration of 3 doses of cabotegravir 150 mg orally every 12 hours resulted in a geometric mean Cmax approximately 2.8-, 5.4-, and 5.6-fold above the geometric mean steady-state Cmax associated with the recommended 30‑mg dose of oral cabotegravir, the recommended 400‑mg dose given monthly, and the recommended 600-mg dose given every 2 months of cabotegravir extended-release injectable suspension, respectively.

At the recommended dose of rilpivirine 25 mg orally once daily, the QT interval is not prolonged to any clinically relevant extent. The rilpivirine 25-mg once-daily mean steady-state Cmax was 247 ng/mL, which is 1.7-fold higher than the mean steady-state Cmax observed with the recommended 600-mg dose of rilpivirine extended-release injectable suspension given monthly and 1.6-fold higher than the mean steady-state Cmax observed with the recommended 900-mg dose of rilpivirine extended-release injectable suspension given every 2 months.

When rilpivirine 75-mg and 300-mg once-daily oral doses (3 and 12 times, respectively, the recommended oral lead-in dosage) were studied in healthy adults, the maximum mean time-matched (95% upper confidence bound) differences in QTcF interval were 10.7 (15.3) and 23.3 (28.4) msec, respectively, after baseline and placebo adjustment. Steady-state administration of rilpivirine 75 mg once daily and 300 mg once daily resulted in a mean steady-state Cmax approximately 4.4- and 11.6-fold, respectively, higher than the mean steady-state Cmax observed with the recommended 600-mg dose of rilpivirine extended-release injectable suspension given monthly and approximately 4.1- and 10.7-fold, respectively, higher than the mean steady-state Cmax observed with the recommended 900-mg dose of rilpivirine extended-release injectable suspension given every 2 months. The corresponding Cmax ratios are 2.6 and 6.7 when compared with the recommended oral rilpivirine dosage [see Warnings and Precautions (5.5)].

12.3 Pharmacokinetics

Absorption, Distribution, and Elimination

The pharmacokinetic properties of the components of CABENUVA are provided in Table 9. The multiple-dose pharmacokinetic parameters are provided in Table 10. For the pharmacokinetic properties of oral cabotegravir and oral rilpivirine, refer to the full prescribing information for VOCABRIA (cabotegravir) and EDURANT (rilpivirine), respectively.

Table 9. Pharmacokinetic Properties of the Components of CABENUVA
 | Cabotegravir | Rilpivirine
Absorptiona
Tmax (days), median | 7 | 3 to 4
Distribution
% Bound to human plasma proteins | >99.8 | 99.7
Blood-to-plasma ratio | 0.52 | 0.7
CSF-to-plasma concentration ratio (median [range])b | 0.003 | 0.01
 | (0.002 to 0.004) | (BLQ to 0.02)
Elimination
t1/2 (weeks), meanc | 5.6 to 11.5 | 13 to 28
Metabolism
Metabolic pathways | UGT1A1 | CYP3A
 | UGT1A9 (minor)
Excretion
Major route of elimination | Metabolism | Metabolism
% of dose excreted as total ^14C (unchanged drug) in urined | 27 (0) | 6 (<1)
% of dose excreted as total ^14C (unchanged drug) in fecesd | 59 (47) | 85 (26)
CSF = Cerebrospinal Fluid, BLQ = Below Limit of Quantification.
a When taken orally with a high-fat meal versus fasted, the AUC(0-inf) (geometric mean ratio [90% CI] of cabotegravir and rilpivirine are 1.14 [1.02, 1.28] and 1.72 [1.36, 2.16]), respectively.
b The clinical relevance of CSF-to-plasma concentration ratios is unknown. Concentrations were measured at steady-state 1 week after intramuscular administration of cabotegravir and rilpivirine extended-release injectable suspensions given monthly or every 2 months.
c Elimination half-life driven by slow absorption rate from the intramuscular injection site.
d Dosing in mass balance studies: single-dose oral administration of [^14C] cabotegravir; single-dose oral administration of [^14C] rilpivirine.

Table 10. Pharmacokinetic Parameters following Once-Daily Oral Cabotegravir and Rilpivirine and following Initiation and Monthly and Every-2-Month Continuation Intramuscular Injections of the Components of CABENUVA in Adults
Drug | Dosing Phase | Dosage Regimen | Geometric Mean (5th, 95th Percentile)a
Drug | Dosing Phase | Dosage Regimen | AUC(0-tau)b (mcg•h/mL) | Cmax (mcg/mL) | Ctaub (mcg/mL)
Cabotegravir | Oral lead-inc | 30 mg once daily | 145; (93.5, 224) | 8.0; (5.3, 11.9) | 4.6; (2.8, 7.5)
Cabotegravir | Initial injection (after oral lead-in)d | 600 mg IM initial dose | 1,591; (714; 3,245) | 8.0; (5.3, 11.9) | 1.5; (0.65, 2.9)
Cabotegravir | Initial injection (direct to injection)e | 600 mg IM initial dose | — | 1.89 (0.438, 5.69) | 1.43 (0.403, 3.90)
Cabotegravir | Monthly injectionf | 400 mg IM monthly | 2,415; (1,494; 3,645) | 4.2; (2.5, 6.5) | 2.8; (1.7, 4.6)
Cabotegravir | Every-2-month injectionf | 600 mg IM; every 2 months | 3,764; (2,431; 5,857) | 4.0; (2.3, 6.8) | 1.6; (0.8, 3.0)
Drug | Dosing Phase | Dosage Regimen | Geometric Mean (5th, 95th Percentile)a
Drug | Dosing Phase | Dosage Regimen | AUC(0-tau)b (ng•h/mL) | Cmax (ng/mL) | Ctaub (ng/mL)
Rilpivirine | Oral lead-inc,g | 25 mg once daily | 2,083; (1,125; 3,748) | 116; (48.6, 244) | 79.4; (31.8, 177)
Rilpivirine | Initial injection (after oral lead-in)d | 900 mg IM initial dose | 44,842; (21,712; 87,575) | 144; (93.9, 221) | 41.9; (21.7, 78.9)
Rilpivirine | Initial injection (direct to injection)e | 900 mg IM initial dose | — | 68 (27.5, 220) | 48.9 (17.7, 138)
Rilpivirine | Monthly injectionf | 600 mg IM monthly | 68,324; (39,042; 118,111) | 121; (68.1, 210) | 85.8; (49.6, 147)
Rilpivirine | Every-2-month injectionf | 900 mg IM every 2 months | 132,450 (76,638; 221,783) | 138 (80.6, 228) | 68.9 (38.0, 119)
IM = Intramuscular.
a Pharmacokinetic parameter values were based on individual post-hoc estimates from separate cabotegravir and rilpivirine population pharmacokinetic models (cabotegravir: pooled FLAIR and ATLAS for the oral, initial, and monthly injection dosing schedule and ATLAS-2M [participants with no prior exposure to cabotegravir plus rilpivirine] for the every-2-month injection dosing schedule; rilpivirine: pooled FLAIR, ATLAS, and ATLAS-2M [participants with no prior exposure], except for initial injection (direct to injection) [see footnote e] and for oral rilpivirine [see footnote g]).
b tau is dosing interval: 24 hours for oral cabotegravir and rilpivirine, 1 month for cabotegravir and rilpivirine extended-release injectable suspensions given monthly, 2 months for cabotegravir and rilpivirine extended-release injectable suspensions given every 2 months.
c Oral lead-in pharmacokinetic parameter values represent steady-state.
d Initial injection Cmax values primarily reflect oral dosing because the initial injection was administered on the same day as the last oral dose; however, AUC(0-tau) and the Ctau values reflect the initial injections for cabotegravir and rilpivirine.
e Pharmacokinetic parameters for initial injection (direct to injection) based on observed data from FLAIR Extension Phase (n = 110), AUC not calculated based on observed data, Cmax = 1 week following initial injection, Ctau = 1 month following initial injection.
f Monthly and every-2-month injection pharmacokinetic parameter values represent Week 48 data.
g Oral rilpivirine: AUC(0-tau) based on population pharmacokinetic estimates of rilpivirine 25 mg once daily from pooled Phase 3 trials with EDURANT (rilpivirine); Ctau based on observed data from FLAIR, ATLAS, and ATLAS-2M; Cmax based on observed data for rilpivirine 25 mg once daily from a pharmacokinetic substudy in pooled Phase 3 trials with EDURANT (rilpivirine).

Specific Populations

No clinically significant differences in the pharmacokinetics of cabotegravir or rilpivirine were observed based on age, sex, race/ethnicity, BMI, or UGT1A1 polymorphisms.

Cabotegravir and rilpivirine concentrations in participants who were hepatitis C virus antibody positive at baseline were similar to those in the overall study population. The effect of hepatitis B virus co-infection on the pharmacokinetics of cabotegravir is unknown. No clinically relevant differences in the pharmacokinetics of oral rilpivirine have been observed with hepatitis B and/or C virus co-infection.

Patients with Renal Impairment: With oral cabotegravir, no clinically significant differences in the pharmacokinetics of cabotegravir are expected in patients with mild, moderate, or severe renal impairment. Cabotegravir has not been studied in patients with end-stage renal disease not on dialysis. As cabotegravir is >99% protein bound, dialysis is not expected to alter exposures of cabotegravir [see Use in Specific Populations (8.6)].

Population pharmacokinetic analyses indicated that mild renal impairment had no clinically relevant effect on the exposure of oral rilpivirine. There is limited or no information regarding the pharmacokinetics of rilpivirine in patients with moderate or severe renal impairment or end-stage renal disease not on dialysis. As rilpivirine is >99% protein bound, dialysis is not expected to alter exposures of rilpivirine [see Use in Specific Populations (8.6)].

Patients with Hepatic Impairment: No clinically significant differences in the pharmacokinetics of cabotegravir are expected in mild to moderate (Child-Pugh A or B) hepatic impairment. The effect of severe hepatic impairment (Child-Pugh C) on the pharmacokinetics of cabotegravir has not been studied [see Use in Specific Populations (8.7)].

No clinically significant differences in the pharmacokinetics of rilpivirine were observed in mild to moderate (Child-Pugh A or B) hepatic impairment. The effect of severe hepatic impairment (Child-Pugh C) has not been studied [see Use in Specific Populations (8.7)].

Geriatric Patients: The pharmacokinetics of cabotegravir (oral or injectable) and of injectable rilpivirine have not been studied and data are limited in participants aged 65 years or older [see Use in Specific Populations (8.5)].

Pediatric Patients: Population pharmacokinetic analyses revealed no clinically relevant differences in exposure between adolescent participants (weighing ≥35 kg and aged at least 12 years) and adult participants with and without HIV-1 from the cabotegravir or rilpivirine development program.

Table 11. Pharmacokinetic Parameters following Cabotegravir and Rilpivirine Orally Once Daily, and Initiation, Monthly, and Every-2-Months Continuation Intramuscular Injections in Adolescents Aged 12 to Younger than 18 Years (≥35 kg)
Drug | Dosing Phase | Dosage Regimen | Geometric Mean (5th, 95th Percentile)a
Drug | Dosing Phase | Dosage Regimen | AUC(0-tau)b (mcg•h/mL) | Cmax (mcg/mL) | Ctaub (mcg/mL)
Cabotegravir | Oral lead-inc | 30 mg once daily | 203 (136, 320) | 10.7 (7.36, 16.6) | 6.43 (4.15, 10.5)
Cabotegravir | Initial injectiond | 600 mg IM initial dose | 2,085 (1,056; 4,259) | 10.8 (7.42, 16.6) | 1.88 (0.801, 3.71)
Cabotegravir | Every-1-month injectione | 400 mg IM every 1 month | 3,416; (2,303; 5,109) | 5.73; (3.76, 8.90) | 4.24; (2.74, 6.45)
Cabotegravir | Every-2-months injectione | 600 mg IM every 2 months | 5,184 (3,511; 7,677) | 5.10 (3.06, 8.24) | 2.54 (1.25, 4.19)
Drug | Dosing Phase | Dosage Regimen | Geometric Mean (5th, 95th Percentile)a
Drug | Dosing Phase | Dosage Regimen | AUC(0-tau)b (ng•h/mL) | Cmax (ng/mL) | Ctaub (ng/mL)
Rilpivirine | Oral lead-inc | 25 mg PO once daily | 2,389 (1,259; 4,414) | 144 (80.8, 234) | 76.1 (27.9, 184)
Rilpivirine | Initial injectiond | 900 mg IM initial dose | 35,259 (20,301; 63,047) | 135 (85.8, 211) | 36.5 (22.4, 59.4)
Rilpivirine | Every-1-month injectione | 600 mg IM every month | 84,280 (49,444; 156,987) | 146 (84.8, 269) | 109 (64.8, 202)
Rilpivirine | Every-2-months injectione | 900 mg IM every 2 months | 110,686 (78,480; 151,744) | 108 (68.0, 164) | 61.8 (44.5, 88.0)
IM = Intramuscular, PO = By Mouth.
a Pharmacokinetic parameter values for cabotegravir were based on individual post-hoc estimates from population pharmacokinetic models in both adolescents with HIV-1 (n = 147) weighing 35.2 to 98.5 kg and adolescents without HIV-1 (n = 62) weighing 39.9 to 167 kg. Pharmacokinetic parameter values for rilpivirine were based on individual post-hoc estimates from a population pharmacokinetic model in adolescents with HIV-1 (n = 148) weighing 35.2 to 98.5 kg.
b tau is dosing interval: 24 hours for oral administration, 1 month for the initial injection and monthly intramuscular injections, and 2 months for every-2-months intramuscular injections of extended‑release injectable suspension.
c Oral lead-in pharmacokinetic parameter values represent steady-state.
d Initial injection Cmax values primarily reflect oral dosing because the initial injection was administered on the same day as the last oral dose; however, the AUC(0-tau) and Ctau values reflect the initial injection.
e Monthly and every-2-month injection pharmacokinetic parameter values represent Week 48 data.

Drug Interaction Studies

Cabotegravir is not a clinically relevant inhibitor of the following enzymes and transporters: CYP1A2, 2A6, 2B6, 2C8, 2C9, 2C19, 2D6, and 3A4; UGT1A1, 1A3, 1A4, 1A6, 1A9, 2B4, 2B7, 2B15, and 2B17; P-glycoprotein (P‑gp); breast cancer resistance protein (BCRP); bile salt export pump (BSEP); organic cation transporter (OCT)1, OCT2; organic anion transporter polypeptide (OATP)1B1, OATP1B3; multidrug and toxin extrusion transporter (MATE) 1, MATE 2-K; and multidrug resistance protein (MRP)2 or MRP4.

In vitro, cabotegravir inhibited renal OAT1 (IC50 = 0.81 microM) and OAT3 (IC50 = 0.41 microM). Based on physiologically based pharmacokinetic (PBPK) modeling, cabotegravir may increase the AUC of OAT1/3 substrates up to approximately 80%.

In vitro, cabotegravir did not induce CYP1A2, CYP2B6, or CYP3A4.

‎Simulations using PBPK modeling show that no clinically significant interaction is expected during coadministration of cabotegravir with drugs that inhibit UGT1A1.

In vitro, cabotegravir was not a substrate of OATP1B1, OATP1B3, OATP2B1, or OCT1.

Cabotegravir is a substrate of P-gp and BCRP in vitro; however, because of its high permeability, no alteration in cabotegravir absorption is expected with coadministration of P-gp or BCRP inhibitors.

Rilpivirine is not likely to have a clinically relevant effect on the exposure of drugs metabolized by CYP enzymes.

Drug interaction studies were not conducted with injectable cabotegravir or injectable rilpivirine. Drug interaction studies with oral cabotegravir or oral rilpivirine are summarized in Tables 12, 13, 14, and 15.

Table 12. Effect of Coadministered Drugs on the Pharmacokinetics of Cabotegravir
Coadministered Drug(s) and Dose(s) | Dose of Cabotegravir | n | Geometric Mean Ratio (90% CI) of Cabotegravir Pharmacokinetic Parameters with/without Coadministered Drugs No Effect = 1.00
Coadministered Drug(s) and Dose(s) | Dose of Cabotegravir | n | Cmax | AUC | Ctau or C24
Etravirine | 30 mg | 12 | 1.04 | 1.01 | 1.00
200 mg twice daily | once daily |  | (0.99, 1.09) | (0.96, 1.06) | (0.94, 1.06)
Rifabutin | 30 mg | 12 | 0.83 | 0.79 | 0.74
300 mg once daily | once daily |  | (0.76, 0.90) | (0.74, 0.83) | (0.70, 0.78)
Rifampin | 30-mg | 15 | 0.94 | 0.41 | 0.50
600 mg once daily | single dose |  | (0.87, 1.02) | (0.36, 0.46) | (0.44, 0.57)
Rilpivirine | 30 mg | 11 | 1.05 | 1.12 | 1.14
25 mg once daily | once daily |  | (0.96, 1.15) | (1.05, 1.19) | (1.04, 1.24)
n = Maximum number of participants with data, CI = Confidence Interval.

Table 13. Effect of Coadministered Drugs on the Pharmacokinetics of Rilpivirine
Coadministered Drug(s) and Dose(s) | Dose of Rilpivirine | n | Geometric Mean Ratio (90% CI) of Rilpivirine Pharmacokinetic Parameters with/without Coadministered Drugs No Effect = 1.00
Coadministered Drug(s) and Dose(s) | Dose of Rilpivirine | n | Cmax | AUC | Cmin
Acetaminophen | 150 mg | 16 | 1.09 | 1.16 | 1.26
500-mg single dose | once dailya |  | (1.01 to 1.18) | (1.10 to 1.22) | (1.16 to 1.38)
Atorvastatin | 150 mg | 16 | 0.91 | 0.90 | 0.90
40 mg once daily | once dailya |  | (0.79 to 1.06) | (0.81 to 0.99) | (0.84 to 0.96)
Chlorzoxazone | 150 mg | 16 | 1.17 | 1.25 | 1.18
500-mg single dose taken 2 hours after rilpivirine | once dailya |  | (1.08 to 1.27) | (1.16 to 1.35) | (1.09 to 1.28)
Darunavir/ritonavir | 150 mg | 14 | 1.79 | 2.30 | 2.78
800/100 mg once daily | once dailya |  | (1.56 to 2.06) | (1.98 to 2.67) | (2.39 to 3.24)
Didanosine | 150 mg | 21 | 1.00 | 1.00 | 1.00
400 mg once daily delayed-release capsules taken 2 hours before rilpivirine | once dailya |  | (0.90 to 1.10) | (0.95 to 1.06) | (0.92 to 1.09)
Ethinyl estradiol/ norethindrone | 25 mg once daily | 15 | ↔b | ↔b | ↔b
0.035 mg once daily/1 mg once daily
Ketoconazole | 150 mg | 15 | 1.30 | 1.49 | 1.76
400 mg once daily | once dailyb |  | (1.13 to 1.48) | (1.31 to 1.70) | (1.57 to 1.97)
Lopinavir/ritonavir | 150 mg | 15 | 1.29 | 1.52 | 1.74
400/100 mg twice daily (soft gel capsule) | once dailya |  | (1.18 to 1.40) | (1.36 to 1.70) | (1.46 to 2.08)
Methadone | 25 mg | 12 | ↔b | ↔b | ↔b
60 to 100 mg once daily, individualized dose | once daily
Raltegravir | 25 mg | 23 | 1.12 | 1.12 | 1.03
400 mg twice daily | once daily |  | (1.04 to 1.20) | (1.05 to 1.19) | (0.96 to 1.12)
Rifabutin | 25 mg | 18 | 0.69 | 0.58 | 0.52
300 mg once daily | once daily |  | (0.62 to 0.76) | (0.52 to 0.65) | (0.46 to 0.59)
Rifabutin; 300 mg once daily | 50 mg; once daily | 18 | 1.43; (1.30 to 1.56) | 1.16; (1.06 to 1.26) | 0.93; (0.85 to 1.01)
 |  |  | (reference arm for comparison was 25 mg once-daily rilpivirine administered alone)
Rifampin | 150 mg | 16 | 0.31 | 0.20 | 0.11
600 mg once daily | once dailya |  | (0.27 to 0.36) | (0.18 to 0.23) | (0.10 to 0.13)
Sildenafil | 75 mg | 16 | 0.92 | 0.98 | 1.04
50-mg single dose | once dailya |  | (0.85 to 0.99) | (0.92 to 1.05) | (0.98 to 1.09)
Tenofovir disoproxil fumarate | 150 mg; once dailya | 16 | 0.96 | 1.01 | 0.99
300 mg once daily |  |  | (0.81 to 1.13) | (0.87 to 1.18) | (0.83 to 1.16)
N = Maximum number of participants with data, CI = Confidence Interval, ↔ = No Change.
a This interaction study has been performed with a dose higher than the recommended dose for rilpivirine (25 mg once daily) assessing the maximal effect on the coadministered drug.
b Comparison based on historic controls.

Table 14. Effect of Cabotegravir on the Pharmacokinetics of Coadministered Drugs
Coadministered Drug(s) and Dose(s) | Dose of Cabotegravir | n | Geometric Mean Ratio (90% CI) of Pharmacokinetic Parameters of Coadministered Drug with/without Cabotegravir; No Effect = 1.00
Coadministered Drug(s) and Dose(s) | Dose of Cabotegravir | n | Cmax | AUC | Ctau or C24
Ethinyl estradiol | 30 mg | 19 | 0.92 | 1.02 | 1.00
0.03 mg once daily | once daily |  | (0.83, 1.03) | (0.97, 1.08) | (0.92, 1.10)
Levonorgestrel | 30 mg | 19 | 1.05 | 1.12 | 1.07
0.15 mg once daily | once daily |  | (0.96, 1.15) | (1.07, 1.18) | (1.01, 1.15)
Midazolam | 30 mg | 12 | 1.09 | 1.10 | NA
3 mg | once daily |  | (0.94, 1.26) | (0.95, 1.26)
Rilpivirine | 30 mg | 11 | 0.96 | 0.99 | 0.92
25 mg once daily | once daily |  | (0.85, 1.09) | (0.89, 1.09) | (0.79, 1.07)
n = Maximum number of participants with data, CI = Confidence Interval, NA = Not Available.

Table 15. Effect of Rilpivirine on the Pharmacokinetics of Coadministered Drugs
Coadministered Drug(s) and Dose(s) | Dose of Rilpivirine | n | Geometric Mean Ratio (90% CI) of Coadministered Drug Pharmacokinetic Parameters with/without EDURANT No Effect = 1.00
Coadministered Drug(s) and Dose(s) | Dose of Rilpivirine | n | Cmax | AUC | Cmin
Acetaminophen | 150 mg | 16 | 0.97 | 0.91 | NA
500-mg single dose | once dailya |  | (0.86 to 1.10) | (0.86 to 0.97)
Atorvastatin | 150 mg | 16 | 1.35 | 1.04 | 0.85
40 mg once daily | once dailya |  | (1.08 to 1.68) | (0.97 to 1.12) | (0.69 to 1.03)
2-hydroxy-atorvastatin |  |  | 1.58 | 1.39 | 1.32
 |  |  | (1.33 to 1.87) | (1.29 to 1.50) | (1.10 to 1.58)
4-hydroxy-atorvastatin |  |  | 1.28 | 1.23 | NA
 |  |  | (1.15 to 1.43) | (1.13 to 1.33)
Chlorzoxazone | 150 mg | 16 | 0.98 | 1.03 | NA
500-mg single dose taken 2 hours after rilpivirine | once dailya |  | (0.85 to 1.13) | (0.95 to 1.13)
Darunavir/ritonavir | 150 mg | 15 | 0.90 | 0.89 | 0.89
800/100 mg once daily | once dailya |  | (0.81 to 1.00) | (0.81 to 0.99) | (0.68 to 1.16)
Didanosine | 150 mg | 13 | 0.96 | 1.12 | NA
400 mg once daily delayed-release capsules taken 2 hours before rilpivirine | once dailya |  | (0.80 to 1.14) | (0.99 to 1.27)
Digoxin | 25 mg | 22 | 1.06 | 0.98 | NA
0.5-mg single dose | once daily |  | (0.97 to 1.17) | (0.93 to 1.04)b
Ethinyl estradiol | 25 mg | 17 | 1.17 | 1.14 | 1.09
0.035 mg once daily | once daily |  | (1.06 to 1.30) | (1.10 to 1.19) | (1.03 to 1.16)
Norethindrone |  |  | 0.94 | 0.89 | 0.99
1 mg once daily |  |  | (0.83 to 1.06) | (0.84 to 0.94) | (0.90 to 1.08)
Ketoconazole | 150 mg | 14 | 0.85 | 0.76 | 0.34
400 mg once daily | once dailya |  | (0.80 to 0.90) | (0.70 to 0.82) | (0.25 to 0.46)
Lopinavir/ritonavir | 150 mg | 15 | 0.96 | 0.99 | 0.89
400/100 mg twice daily (soft gel capsule) | once dailya |  | (0.88 to 1.05) | (0.89 to 1.10) | (0.73 to 1.08)
Methadone | 25 mg | 13
60 to 100 mg once daily, individualized dose | once daily
R(‑) methadone |  |  | 0.86 | 0.84 | 0.78
 |  |  | (0.78 to 0.95) | (0.74 to 0.95) | (0.67 to 0.91)
S(+) methadone |  |  | 0.87 | 0.84 | 0.79
 |  |  | (0.78 to 0.97) | (0.74 to 0.96) | (0.67 to 0.92)
Metformin | 25 mg | 20 | 1.02 | 0.97 | NA
850-mg single dose | once daily |  | (0.95 to -1.10) | (0.90 to 1.06)c
Raltegravir | 25 mg | 23 | 1.10 | 1.09 | 1.27
400 mg twice daily | once daily |  | (0.77 to 1.58) | (0.81 to 1.47) | (1.01 to 1.60)
Rifampin | 150 mg | 16 | 1.02 | 0.99 | NA
600 mg once daily | once dailya |  | (0.93 to 1.12) | (0.92 to 1.07)
25-desacetylrifampin |  |  | 1.00 | 0.91 | NA
 |  |  | (0.87 to 1.15) | (0.77 to 1.07)
Sildenafil | 75 mg | 16 | 0.93 | 0.97 | NA
50-mg single dose | once dailya |  | (0.80 to 1.08) | (0.87 to 1.08)
N-desmethyl-sildenafil |  |  | 0.90 | 0.92 | NA
 |  |  | (0.80 to 1.02) | (0.85 to 0.99)b
Tenofovir disoproxil | 150 mg | 16 | 1.19 | 1.23 | 1.24
fumarate | once dailya |  | (1.06 to 1.34) | (1.16 to 1.31) | (1.10 to 1.38)
300 mg once daily
n = Maximum number of participants with data, CI = Confidence Interval, NA = Not Available.
a This interaction study has been performed with a dose higher than the recommended dose for rilpivirine (25 mg once daily) assessing the maximal effect on the coadministered drug.
b AUC(0-last)
c n = (maximum number of participants with data) for AUC(0-∞) = 15.

12.4 Microbiology

Mechanism of Action

Cabotegravir inhibits HIV integrase by binding to the integrase active site and blocking the strand transfer step of retroviral deoxyribonucleic acid (DNA) integration that is essential for the HIV replication cycle. The mean 50% inhibitory concentration (IC50) value of cabotegravir in a strand transfer assay using purified recombinant HIV-1 integrase was 3.0 nM.

Rilpivirine is a diarylpyrimidine NNRTI of HIV-1 and inhibits HIV-1 replication by non-competitive inhibition of HIV-1 reverse transcriptase (RT). Rilpivirine does not inhibit the human cellular DNA polymerases α, β, and γ.

Antiviral Activity in Cell Culture

Cabotegravir exhibited antiviral activity against laboratory strains of HIV-1 (subtype B, n = 4) with mean 50 percent effective concentration (EC50) values of 0.22 to 1.7 nM in peripheral blood mononuclear cells (PBMCs) and 293 cells. Cabotegravir demonstrated antiviral activity in PBMCs against a panel of 24 HIV-1 clinical isolates (3 in each of group M subtypes A, B, C, D, E, F, and G and 3 in group O) with a median EC50 value of 0.19 nM (range: 0.02 to 1.06 nM, n = 24). The median EC50 value against subtype B clinical isolates was 0.05 nM (range: 0.02 to 0.50 nM, n = 3). Against clinical HIV-2 isolates, the median EC50 value was 0.12 nM (range: 0.10 to 0.14 nM, n = 3).

Rilpivirine exhibited activity against laboratory strains of wild-type HIV-1 in an acutely infected T-cell line with a median EC50 value for HIV-1IIIB of 0.73 nM (0.27 ng/mL). Rilpivirine demonstrated antiviral activity against a broad panel of HIV-1 group M (subtypes A, B, C, D, F, G, and H) primary isolates with EC50 values ranging from 0.07 nM to 1.01 nM (0.03 to 0.37 ng/mL) and was less active against group O primary isolates with EC50 values ranging from 2.88 nM to 8.45 nM (1.06 to 3.10 ng/mL).

In cell culture, cabotegravir was not antagonistic in combination with the NNRTI rilpivirine, or the nucleoside reverse transcriptase inhibitors (NRTIs) emtricitabine (FTC), lamivudine (3TC), or tenofovir disoproxil fumarate (TDF).

The antiviral activity of rilpivirine was not antagonistic when combined with the NNRTIs efavirenz, etravirine, or nevirapine; the NRTIs abacavir, didanosine, emtricitabine, lamivudine, stavudine, tenofovir, or zidovudine; the protease inhibitors amprenavir, atazanavir, darunavir, indinavir, lopinavir, nelfinavir, ritonavir, saquinavir, or tipranavir; the fusion inhibitor enfuvirtide; the CCR5 co-receptor antagonist maraviroc, or the INSTI raltegravir.

Resistance

Cell Culture: Cabotegravir-resistant viruses were selected during passage of HIV-1 strain IIIB in MT-2 cells in the presence of cabotegravir. Amino acid substitutions in integrase that emerged and conferred decreased susceptibility to cabotegravir included Q146L (fold change: 1.3 to 4.6), S153Y (fold change: 2.8 to 8.4), and I162M (fold change: 2.8). The integrase substitution T124A also emerged alone (fold change: 1.1 to 7.4 in cabotegravir susceptibility), in combination with S153Y (fold change: 3.6 to 6.6 in cabotegravir susceptibility) or I162M (2.8-fold change in cabotegravir susceptibility). Cell culture passage of virus harboring integrase substitutions Q148H, Q148K, or Q148R selected for additional substitutions (C56S, V72I, L74M, V75A, T122N, E138K, G140S, G149A, and M154I), with substituted viruses having reduced susceptibility to cabotegravir of 2.0- to 410-fold change. The combinations of E138K+Q148K and V72I+E138K+Q148K conferred the greatest reductions of 53- to 260‑fold change and 410-fold change, respectively.

Rilpivirine-resistant strains were selected in cell culture starting from wild-type HIV-1 of different origins and subtypes as well as NNRTI-resistant HIV-1. The frequently observed amino acid substitutions that emerged and conferred decreased phenotypic susceptibility to rilpivirine included L100I; K101E; V106I and A; V108I; E138K and G, Q, R; V179F and I; Y181C and I; V189I; G190E; H221Y; F227C; and M230I and L.

Clinical Trials: In the pooled Phase 3 FLAIR (Week 124) and ATLAS (Week 96) analysis, there were 8 confirmed virologic failures (2 consecutive HIV-1 RNA ≥200 copies/mL) on cabotegravir plus rilpivirine (8/591, 1.4%) and 8 confirmed virologic failures on current antiretroviral regimen (8/591, 1.4%). Of the 8 confirmed virologic failures in the cabotegravir plus rilpivirine arm, 7 (88%) had treatment-emergent NNRTI resistance-associated substitutions K101E, V106V/A, V108I, E138A, E138G, E138K, H221H/L, or M230L in reverse transcriptase, and 6 of them showed reduced phenotypic susceptibility to rilpivirine (range: 2- to 27-fold). One additional participant in the ATLAS Extension Switch on cabotegravir plus rilpivirine had emergent NNRTI resistance substitution E138A at Week 80 with HIV-1 RNA >50 copies/mL and <200 copies/mL.

Additionally, 5 of the 8 (63%) cabotegravir plus rilpivirine confirmed virologic failures had treatment-emergent INSTI resistance-associated substitutions and reduced phenotypic susceptibility to cabotegravir: Q148R (n = 2; 5- and 9-fold decreased susceptibility to cabotegravir), G140R (n = 1; 7-fold decreased susceptibility to cabotegravir), N155H (n = 1; 3‑fold decreased susceptibility to cabotegravir), or N155H+R263K (n = 1; 9-fold decreased susceptibility to cabotegravir).

There was another confirmed virologic failure participant at Week 112 in FLAIR who had switched to cabotegravir plus rilpivirine direct to injection at Week 100; there were no INSTI resistance‑associated substitutions detected at failure.

In comparison, in the current antiretroviral regimen arm with 8 confirmed virologic failures, 2 of 7 (29%) who had post-baseline resistance data had treatment-emergent resistance substitutions and phenotypic resistance to their antiretroviral drugs; both had treatment-emergent NRTI substitutions, M184V or I, which conferred resistance to emtricitabine or lamivudine in their regimen, and one of them also had the treatment-emergent NNRTI resistance substitution G190S, which conferred resistance to efavirenz in their regimen.

In the ATLAS-2M trial, there were 11 confirmed virologic failures (2 consecutive HIV-1 RNA ≥200 copies/mL) through Week 48: 9 participants (1.7%) in the every-2-month treatment arm and 2 participants (0.4%) in the monthly treatment arm. Of note, 8 of the 11 (73%) participants met confirmed virologic failure criteria at or before the Week 24 injection visit.

Four of the 9 confirmed virologic failure participants in the every-2-month arm transitioned from the oral current antiretroviral regimen arm of ATLAS into this trial.

In the every-2-month treatment arm, 8 of 9 (89%) confirmed virologic failure participants had NNRTI resistance-associated substitutions (E138E/K+V179V/I, K101E+E138A, A98G+K103N, E138K, V179I+Y188L+P225H, Y188L, K103N+E138A, or K101E) at virologic failure. Decreases in rilpivirine susceptibility for these 8 participant isolates ranged from 2- to 30-fold. Six of the 8 participants with NNRTI resistance-associated substitutions also had INSTI resistance-associated substitutions (L74I+Q148Q/R+N155N/H (n = 2), L74I+T97A+N155H, L74I+N155H, N155H, or L74I+Q148R) at failure with cabotegravir fold changes ranging from 1- to 9-fold. The INSTI polymorphism L74I was detected at baseline in 5 of the virologic failure participants by a HIV-1 proviral DNA assay.

In the monthly treatment arm, both of the confirmed virologic failure participants had NNRTI resistance-associated substitutions (K101E+M230L or Y188F+G190Q) at virologic failure with decreased susceptibility to rilpivirine of 17- and >119.2-fold, respectively. Both participants also had INSTI resistance-associated substitutions (N155N/H or Q148R+E138E/K) at failure with decreased susceptibility to cabotegravir of 2- and 5-fold, respectively. Neither participant had the L74I integrase polymorphism at baseline.

Genotypic Baseline Factors Associated with Virologic Failure

An increased risk of cabotegravir plus rilpivirine confirmed virologic failure is associated with baseline virological factors: HIV-1 subtype A1, the presence of baseline integrase L74I polymorphism, and archived NNRTI resistance-associated substitutions.

Association of Subtype A1 and Baseline L74I Polymorphism in Integrase with Cabotegravir plus Rilpivirine Virologic Failure

Eight of the 18 (44%) cabotegravir plus rilpivirine confirmed virologic failures in FLAIR, ATLAS, and ATLAS-2M had HIV‑1 subtype A1 with 7 of the 8 subtype A1 failures having the integrase polymorphism L74I detected at baseline and failure timepoints (Table 16). There was no detectable phenotypic resistance to cabotegravir conferred by the presence of L74I at baseline. Subtype A1 is uncommon in the U.S.

The presence of the integrase polymorphism L74I in subtype B commonly seen in the U.S. was not associated with virologic failure. In contrast to FLAIR and ATLAS, where all virologic failures were subtype A, A1, or AG, subtypes of the cabotegravir plus rilpivirine virologic failures in ATLAS-2M included A (n = 1), A1 (n = 3), B (n = 4), C (n = 2), and complex/A1 (n = 1).

Association of Archived Baseline NNRTI Substitutions with Cabotegravir plus Rilpivirine Virologic Failure

The presence of archived NNRTI resistance-associated substitutions at baseline detected using an exploratory HIV-1 proviral DNA assay was associated with a higher virologic failure rate in the every-2-month arm of ATLAS-2M and in the cabotegravir plus rilpivirine arm (monthly) of ATLAS compared to without archived NNRTI resistance-associated substitutions (Table 16). However, in clinical practice, it is unlikely baseline resistance testing will be performed on virologically suppressed patients (HIV-1 RNA <50 copies/mL). Thus, in patients with an incomplete or uncertain NNRTI treatment history, consideration should be given before starting cabotegravir plus rilpivirine treatment.

Table 16. Rate of Confirmed Virologic Failure in FLAIR, ATLAS, and ATLAS-2M: Baselinea Analysis (Subtype Al, Presence of lntegrase Polymorphism L74I, and Presence of Archived NNRTI Resistance-Associated Substitutions)
 | FLAIR; CAB+RPV; N = 283 | FLAIR; CAR; N = 283 | ATLAS; CAB+RPV; N = 308 | ATLAS; CAR; N = 308 | ATLAS-2M; Q4W; N = 523 | ATLAS-2M; Q8W; N = 522
Total confirmed virologic failures | 5 | 4 | 3 | 4 | 2 | 9
Subtype A1b | 4/8 (50%) | 1/4 (25%) | 1/17 (6%) | 0/21 (0%) | 0/30 (0%) | 4/31 (13%)
+L74Ic | 4/5 (80%) | 1/3 (33%) | 1/16 (6%) | 0/19 (0%) | 2/28 (0%) | 3/26 (12%)
-L74I | 0/3 (0%) | 0/1 (0%) | 0/1 (0%) | 0/2 (0%) | 0/2 (0%) | 1/5 (20%)
Other subtypes | 2/268 (0.7%) | 3/272 (1%) | 2/240 (0.8%) | 4/252 (1.6%) | 2/409 (0.5%) | 5/415 (1.2%)
+L74Ic | 0/49 (0%) | 1/43 (2.3%) | 1/29 (3%) | 1/39 (2.6%) | 0/42 (0%) | 2/48 (4%)
-L74I | 0/219 (2.5%) | 2/229 (0.9%) | 1/211 (0.5%) | 3/213 (1.4%) | 2/367 (0.5%) | 3/367 (0.8%)
Missing data | 7 | 7 | 51 | 35 | 84 | 76
With NNRTI RASd | NA | NA | 3/78 (4%) | 2/83 (2%) | 1/128 (0.8%) | 7/117 (6%)
Without NNRTI RAS | NA | NA | 0/179 (0%) | 2/190 (1%) | 1/310 (0.3%) | 2/327 (0.6%)
Missing data | NA | NA | 51 | 35 | 84 | 76
NNRTI = Non-Nucleoside Reverse Transcriptase Inhibitor, CAB+RPV = Cabotegravir + Rilpivirine, CAR = Current Antiretroviral Regimen, RAS = Resistance-Associated Substitutions, NA = Not Available.
a Baseline and/or Screening result used.
b Per Standard Monogram Nomenclature Reports. Based on June 2020 Los Alamos National Library panel, the majority of HIV-1 subtype A1 was reclassified as HIV-1 subtype A6.
c L74I and L74L/I mixture.
d Baseline/Screening NNRTI substitutions at L100, K101, K103, V106, V108, E138, V179, Y181, Y188, G190, H221, P225, M230.

Cross-Resistance

Virologic failure isolates from cabotegravir plus rilpivirine treatment in FLAIR, ATLAS, and ATLAS-2M exhibited cross-resistance to INSTIs and NNRTIs. All confirmed virologic isolates with genotypic evidence of cabotegravir resistance had cross-resistance to elvitegravir and raltegravir but retained phenotypic susceptibility to dolutegravir and when tested bictegravir. Virologic failure isolates with rilpivirine resistance had cross-resistance with NNRTIs delavirdine, doravirine, efavirenz, etravirine, and nevirapine.

Cabotegravir: Cross-resistance has been observed among INSTIs. Cabotegravir had reduced susceptibility (>5-fold change) to recombinant HIV-1 strain NL432 viruses harboring the following integrase amino acid substitutions: G118R, Q148K, Q148R, T66K+L74M, E92Q+N155H, E138A+Q148R, E138K+Q148K/R, G140C+Q148R, G140S+Q148H/K/R, Y143H+N155H, and Q148R+N155H (range: 5.1- to 81-fold). The substitutions E138K+Q148K and Q148R+N155H conferred the greatest reductions in susceptibility of 81- and 61-fold, respectively.

Cabotegravir was active against viruses harboring the NNRTI substitutions K103N or Y188L, or the NRTI substitutions M184V, D67N/K70R/T215Y, or V75I/F77L/F116Y/Q151M.

Rilpivirine: Cross-resistance has been observed among NNRTIs. The single NNRTI substitutions K101P, Y181I, and Y181V conferred 52-, 15-, and 12-times fold change to rilpivirine, respectively. The K103N substitution did not show reduced susceptibility to rilpivirine by itself. Combinations of 2 or 3 NNRTI resistance-associated substitutions gave 3.7- to 554-fold change to rilpivirine in 38% and 66% of substitutions, respectively. Considering all available cell culture and clinical data, any of the following amino acid substitutions, when present at baseline, are likely to decrease the antiviral activity of rilpivirine: K101E and P; E138A, G, K, R, and Q; V179L; Y181C, I, and V; Y188L; H221Y; F227C; M230I and L, and the combination of L100I/K103N.

13 NONCLINICAL TOXICOLOGY

13.1 Carcinogenesis, Mutagenesis, Impairment of Fertility

Carcinogenesis

Two-year carcinogenicity studies in mice and rats were conducted with cabotegravir. In mice, no drug-related increases in tumor incidence were observed at cabotegravir exposures (AUC) up to approximately 8 times (males) and 7 times (females) higher than those in humans at the RHD. In rats, no drug-related increases in tumor incidence were observed at cabotegravir exposures up to approximately 26 times higher than those in humans at the RHD.

Two-year carcinogenicity studies in mice and rats were conducted with rilpivirine. In mice, rilpivirine was positive for hepatocellular neoplasms in both males and females. The observed hepatocellular findings in mice may be rodent-specific. At the lowest tested dose in the mouse carcinogenicity study, the systemic exposure to rilpivirine was 21 times that observed in humans at the RHD. In rats, no drug-related neoplasms were observed at exposures 3 times those observed in humans at the RHD.

Mutagenesis

Cabotegravir and rilpivirine were not genotoxic in the bacterial reverse mutation assay, mouse lymphoma assay, or in the in vivo rodent micronucleus assay.

Impairment of Fertility

In rats, no effects on fertility were observed at cabotegravir exposures (AUC) >20 times (male) and 28 times (female) the exposure in humans at the RHD. Similarly, no effects on fertility were observed in rats at rilpivirine exposures (AUC) >36 times (male) and 40 times (female) the exposure in humans at the RHD.

14 CLINICAL STUDIES

14.1 Clinical Trials in Adults

Monthly Dosing Trials

The efficacy of CABENUVA has been evaluated in 2 Phase 3 randomized, multicenter, active-controlled, parallel-arm, open-label, non-inferiority trials:

- Trial 201584 (FLAIR [NCT02938520]), (n = 629): antiretroviral treatment (ART)‑naive participants with HIV-1 received a dolutegravir INSTI-containing regimen for 20 weeks (either dolutegravir/abacavir/lamivudine or dolutegravir plus 2 other NRTIs if participants were HLA‑B*5701 positive). Participants who were virologically suppressed (HIV-1 RNA <50 copies/mL, n = 566) were then randomized (1:1) to receive either a cabotegravir plus rilpivirine regimen or remain on the current antiretroviral regimen. Participants randomized to receive cabotegravir plus rilpivirine initiated treatment with daily oral lead-in dosing with one 30-mg VOCABRIA (cabotegravir) tablet plus one 25-mg EDURANT (rilpivirine) tablet for at least 4 weeks followed by monthly injections with CABENUVA for an additional 44 weeks [see Dosage and Administration (2.2, 2.3)].
- Trial 201585 (ATLAS [NCT02951052]), (n = 616): ART-experienced, virologically-suppressed (for at least 6 months; median prior treatment duration was 4.3 years) participants (HIV-1 RNA <50 copies/mL) with HIV-1 were randomized and received either a cabotegravir plus rilpivirine regimen or remained on their current antiretroviral regimen. Participants randomized to receive cabotegravir plus rilpivirine initiated treatment with daily oral lead-in dosing with one 30-mg VOCABRIA (cabotegravir) tablet plus one 25-mg EDURANT (rilpivirine) tablet for at least 4 weeks followed by monthly injections with CABENUVA for an additional 44 weeks [see Dosage and Administration (2.2, 2.3)].

The primary analysis was conducted after all participants completed their Week 48 visit or discontinued the trial prematurely.

At baseline, in FLAIR and ATLAS the median age was 34 years and 40 years, 22% and 32% were female, and 24% and 31% were non-White, respectively. In both studies, 7% had CD4+ cell count <350 cells/mm^3; these characteristics were similar between treatment arms. In ATLAS, participants received an NNRTI (50%), integrase inhibitor (33%), or protease inhibitor (17%) as their baseline third-agent class prior to randomization; this was similar between treatment arms. Participants with hepatitis B co-infection were excluded from the trial.

The primary endpoint of FLAIR and ATLAS was the proportion of participants with plasma HIV-1 RNA ≥50 copies/mL at Week 48.

The primary endpoint and other Week 48 outcomes, including outcomes by key baseline factors, for FLAIR and ATLAS are shown in Tables 17 and 18.

Table 17. Virologic Outcomes of Randomized Treatment in FLAIR and ATLAS Trials at Week 48
Virologic Outcomes | FLAIR Monthly Dosing |  | ATLAS Monthly Dosing
Virologic Outcomes | CAB plus RPV; (n = 283) | CAR; (n = 283) | CAB plus RPV; (n = 308) | CAR; (n = 308)
HIV-1 RNA ≥50 copies/mLa | 2% | 2% | 2% | 1%
Treatment difference | -0.4% |  | 0.7%
 | (95% CI: -2.8%, 2.1%) |  | (95% CI: -1.2%, 2.5%)
HIV-1 RNA <50 copies/mL | 94% | 93% | 93% | 95%
No virologic data at Week 48 window | 4% | 4% | 6% | 4%
Discontinued due to adverse event or death | 3% | <1% | 4% | 2%
Discontinued for other reasons | 1% | 4% | 2% | 2%
Missing data during window but on study | 0 | 0 | 0 | 0
CAB = Cabotegravir, RPV = Rilpivirine, CAR = Current Antiretroviral Regimen, n = Number of participants in each treatment group, CI = Confidence Interval.
a Includes participants who discontinued for lack of efficacy and discontinued while not suppressed.

Adjusted for study and randomization stratification factors, treatment difference of HIV-1 RNA ≥50 copies/mL for the pooled data was 0.2% with 95% CI (-1.4%, 1.7%).

Table 18. Proportion of Participants in FLAIR and ATLAS Trials with Plasma HIV-1 RNA ≥50 copies/mL at Week 48 for Key Baseline Factors
Baseline Factors | FLAIR Monthly Dosing |  | ATLAS Monthly Dosing
Baseline Factors | CAB plus RPV; (N = 283); n/N (%) | CAR; (N = 283); n/N (%) | CAB plus RPV; (N = 308); n/N (%) | CAR; (N = 308); n/N (%)
Baseline CD4+ (cells/mm^3)
<350 | 0/19 | 1/27 (4%) | 0/23 | 1/27 (4%)
≥350 to <500 | 3/64 (5%) | 0/60 | 2/56 (4%) | 0/60
≥500 | 3/200 (2%) | 6/196 (3%) | 3/299 (1%) | 2/224 (<1%)
Gender
Male | 3/220 (1%) | 6/219 (3%) | 3/209 (1%) | 3/204 (1%)
Female | 3/63 (5%) | 1/64 (2%) | 2/99 (2%) | 0/104
Race
White | 6/216 (3%) | 5/201 (2%) | 3/214 (1%) | 2/207 (<1%)
African American/African Heritage | 0/47 | 2/56 (4%) | 2/62 (3%) | 1/77 (1%)
Asian/Other | 0/20 | 0/24 | 0/32 | 0/24
Body mass index
<30 kg/m^2 | 3/243 (1%) | 7/246 (3%) | 3/248 (1%) | 1/242 (<1%)
≥30 kg/m^2 | 3/40 (8%) | 0/37 | 2/60 (3%) | 2/66 (3%)
Age (years)
<50 | 5/250 (2%) | 6/254 (2%) | 4/242 (2%) | 2/212 (<1%)
≥50 | 1/33 (3%) | 1/29 (3%) | 1/66 (2%) | 1/96 (1%)
Baseline antiviral therapy at randomization
Protease inhibitor-containing regimen | 0 | 0 | 1/51 (2%) | 0/54
Integrase inhibitor-containing regimen | 6/283 (2%) | 7/283 (2%) | 0/102 | 2/99 (2%)
Non-nucleoside reverse transcriptase inhibitor-containing regimen | 0 | 0 | 4/155 (3%) | 1/155 (<1%)
CAB = Cabotegravir, RPV = Rilpivirine, CAR = Current Antiretroviral Regimen.

Participants in both the FLAIR and ATLAS trials were virologically suppressed prior to Day 1 or at study entry, respectively, and no clinically relevant change from baseline in CD4+ cell counts was observed.

In FLAIR at Week 96, the proportion of participants with HIV-1 RNA ≥50 copies/mL was 3.2 % for both the cabotegravir plus rilpivirine (n = 283) and current antiretroviral regimen (n = 283) treatment arms; adjusted treatment difference was 0.0% with 95% CI (-2.9%, 2.9%). The proportion of participants with HIV-1 RNA <50 copies/mL was 87% and 89% for the cabotegravir plus rilpivirine and the current antiretroviral regimen arms, respectively; adjusted treatment difference was -2.8% with 95% CI (-8.2%, 2.5%).

Optional Oral Lead-In: FLAIR Extension Phase

In the FLAIR study during the Extension Phase (Week 100 to Week 124), the efficacy of CABENUVA was evaluated in patients who switched (at Week 100) from their current antiretroviral regimen to CABENUVA, with and without an oral lead-in phase. A total of 121 participants chose to start the treatment with oral lead-in and 111 participants chose direct to injection. Participants were not randomized during the Extension Phase. At Week 124, the proportion of participants with HIV-1 RNA ≥50 copies/mL was 0.8% and 0.9% for the oral lead-in and direct to injection groups, respectively. The rates of virologic suppression (HIV-1 RNA <50 copies/mL) were similar in both the oral lead-in (93%) and direct to injection (99%) groups.

Every-2-Month Dosing Trial

The efficacy of CABENUVA dosed every 2 months has been evaluated in 1 Phase 3b randomized, multicenter, parallel-arm, open-label, non-inferiority trial:

- Trial 207966 (ATLAS-2M [NCT03299049]), (n = 1,045): ART‑experienced, virologically suppressed participants with HIV-1, including 504 participants from the ATLAS trial (randomized to CAB plus RPV [n = 253] or CAR [n = 251]; prior exposure to cabotegravir plus rilpivirine [n = 391]), were randomized and received a cabotegravir plus rilpivirine regimen administered as injection doses of cabotegravir 400 mg plus rilpivirine 600 mg either monthly or cabotegravir 600 mg plus rilpivirine 900 mg every 2 months. Participants without prior exposure to cabotegravir plus rilpivirine initiated treatment with daily oral lead-in dosing with one 30-mg VOCABRIA (cabotegravir) tablet plus one 25-mg EDURANT (rilpivirine) tablet for at least 4 weeks followed by monthly or every-2-month injections with CABENUVA for an additional 44 weeks.

The primary analysis was conducted after all participants completed their Week 48 visit or discontinued the study prematurely.

At baseline, the median age was 42 years, 27% were female, 27% were non-White, and 6% had a CD4+ cell count <350 cells per mm3; these characteristics were similar between the treatment arms. Participants received either an NNRTI (29%), an integrase inhibitor besides cabotegravir plus rilpivirine (26%), a protease inhibitor (7%), or cabotegravir plus rilpivirine (37%) as their baseline third-agent class prior to randomization.

The primary endpoint of ATLAS-2M was the proportion of participants with a plasma HIV-1 RNA ≥50 copies/mL at Week 48.

The primary endpoint and other Week 48 outcomes, including outcomes by key baseline factors, for ATLAS-2M are shown in Tables 19 and 20.

Table 19. Virologic Outcomes of Randomized Treatment in ATLAS 2-M Trial at Week 48
Virologic Outcomes | Cabotegravir plus Rilpivirine
Virologic Outcomes | Every-2-Month Dosing; n = 522 | Monthly Dosing; n = 523
HIV-1 RNA ≥50 copies/mLa | 2% | 1%
Treatment difference | 0.8
 | (95% CI: -0.6%, 2.2%)
HIV-1 RNA <50 copies/mL | 94% | 94%
No virologic data at Week 48 window | 4% | 6%
Discontinued study due to adverse event or death | 2% | 3%
Discontinued for other reasons | 2% | 3%
Missing data during window but on study | 0 | 0
a Includes participants who discontinued for lack of efficacy, discontinued while not suppressed.
n = Number of participants in each treatment group, CI = Confidence Interval.

Table 20. Proportion of Participants in ATLAS 2-M Trial with Plasma HIV-1 RNA ≥50 copies/mL at Week 48 for Key Baseline Factors
Baseline Factors | Cabotegravir plus Rilpivirine
Baseline Factors | Every-2-Month Dosing; (N = 522); n/N (%) | Monthly Dosing; (N = 523); n/N (%)
Baseline CD4+ (cells/mm^3)
<350 | 1/35 (3%) | 1/27 (4%)
≥350 to <500 | 1/96 (1%) | 0/89
≥500 | 7/391 (2%) | 4/407 (1%)
Gender
Male | 4/385 (1%) | 5/380 (1%)
Female | 5/137 (4%) | 0/143
Race
White | 5/370 (1%) | 5/393 (1%)
Black/African American; Asian/Other | 4/101 (4%); 0/51 | 0/90; 0/40
Body mass index
<30 kg/m^2 | 3/409 (1%) | 3/425 (1%)
≥30 kg/m^2 | 6/113 (5%) | 2/98 (2%)
Age (years)
<35 | 4/137 (3%) | 1/145 (1%)
35 to <50 | 3/242 (1%) | 2/239 (1%)
≥50 | 2/143 (1%) | 2/139 (1%)
Prior exposure to cabotegravir plus rilpivirine
None | 5/327 (2%) | 5/327 (2%)
1 to 24 Weeks | 3/69 (4%) | 0/68
>24 Weeks | 1/126 (1%) | 0/128
Baseline third-agent class
Protease inhibitor-containing regimen | 1/40 (3%) | 1/30 (3%)
Integrase inhibitor-containing regimen | 3/136 (2%) | 2/141 (1%)
NNRTI-containing regimen | 1/151 (1%) | 2/156 (1%)
Cabotegravir plus rilpivirine | 4/195 (2%) | 0/196

14.2 Clinical Trial in Adolescents

Trial 208580 (MOCHA, [NCT03497676])

The safety, tolerability, and pharmacokinetics of oral and injectable cabotegravir and oral and injectable rilpivirine were assessed in an ongoing Phase 1/2 multicenter, open-label, non‑comparative study, MOCHA (IMPAACT 2017) [see Adverse Reactions (6.1), Clinical Pharmacology (12.3)].

Cohort 1

Fifty-five virologically suppressed adolescents with HIV-1 aged 12 to younger than 18 years and weighing at least 35 kg were enrolled to 1 of 4 subgroups, 1C (Q4W): cabotegravir monthly dosing, 1C (Q8W): cabotegravir every‑2‑month dosing, 1R (Q4W): rilpivirine monthly dosing or 1R (Q8W): rilpivirine every‑2‑month dosing.

In cohort 1C, participants (n = 30) received one 30-mg cabotegravir tablet daily for at least 4 weeks followed by monthly cabotegravir injections for 3 months (Month 1: 600-mg injection, Months 2 and 3: 400-mg injection), or every-2-month cabotegravir injections for 2 months (Months 1 and 2: 600-mg injection), while continuing background antiretroviral therapy. In cohort 1R, participants (n = 25) received one 25-mg rilpivirine tablet daily for at least 4 weeks followed by monthly rilpivirine injections for 3 months (Month 1: 900-mg injection, Months 2 and 3: 600-mg injection), or every-2-month rilpivirine injections for 2 months (Months 1 and 2: 900-mg injection), while continuing background antiretroviral therapy.

At baseline, in cohort 1 (n = 55), the median age of participants was 15.0 years, the median weight was 50.0 kg (range: 37.4, 98.5), 47% were female, 76% were Black/African American, 16% were Asian, 7% were White; and no participant had a CD4+ cell count <350 cells per mm^3. At baseline, median CD4+ cell count was 725 cells per mm^3 (range: 397 to 1808).

The primary objectives at Week 16, which were to confirm the use of the adult dose through the evaluation of safety and pharmacokinetics in virologically suppressed adolescents with HIV-1, were met enabling the progression of participants to cohort 2 [see Adverse Reactions (6.1), Clinical Pharmacology (12.3)].

Cohort 2

Cohort 2 enrolled eligible participants who had completed cohort 1 as well as eligible participants who had not been previously enrolled in the study. Cohort 2 participants (n = 144) discontinued their background antiretroviral therapy and received one 30-mg cabotegravir tablet plus one 25-mg rilpivirine tablet daily for at least 4 weeks followed by every-2-month cabotegravir injections (Months 1 and 2: 600-mg injection, then 600-mg injection once every 2 months) and rilpivirine injections (Months 1 and 2: 900-mg injection, then 900-mg injection once every 2 months).

At baseline, in cohort 2, the median age of participants was 15.0 years, the median weight was 48.5 kg (range: 35.2, 100.9), 51% were female, 74% were Black/African American, 25% were Asian, 1% was White; and 4 participants had a CD4+ cell count less than 350 cells per mm^3. At baseline, median CD4+ cell count was 739.5 cells per mm^3 (range: 81 to 1925).

The primary objective at Week 24, which was to confirm the safety of injectable cabotegravir plus injectable rilpivirine in virologically suppressed adolescents with HIV-1, was met [see Adverse Reactions (6.1)]. Antiviral activity was assessed as a secondary objective: 139 of the 141 (98.6%) participants with available data remained virologically suppressed (HIV-1 RNA <50 copies/mL) at Week 24. The median change from baseline in CD4+ cell count at Week 24 was -36.0 cells per mm^3.

16 HOW SUPPLIED/STORAGE AND HANDLING

How Supplied

CABENUVA is supplied in 2 dosing kits. Each kit contains 1 vial of cabotegravir extended‑release injectable suspension and 1 vial of rilpivirine extended-release injectable suspension, co‑packaged as follows:

CABENUVA 400-mg/600-mg Kit (NDC 49702-253-15) containing:

- One single-dose vial of cabotegravir extended-release injectable suspension containing 400 mg/2 mL (200 mg/mL) of cabotegravir.
- One single-dose vial of rilpivirine extended-release injectable suspension containing 600 mg/2 mL (300 mg/mL) of rilpivirine

CABENUVA 600-mg/900-mg Kit (NDC 49702-240-15) containing:

- One single-dose vial of cabotegravir extended-release injectable suspension containing 600 mg/3 mL (200 mg/mL) of cabotegravir.
- One single-dose vial of rilpivirine extended-release injectable suspension containing 900 mg/3 mL (300 mg/mL) of rilpivirine.

Each dosing kit also contains 2 syringes, 2 syringe labels, 2 vial adapters, and 2 needles for intramuscular injection (23-gauge, 1½ inch). The vial stoppers are not made with natural rubber latex.

Storage and Handling

Store CABENUVA in the refrigerator at 2°C to 8°C (36°F to 46°F) in the original carton until ready to use. Do not freeze. Do not mix with any other product or diluent.

Prior to administration, vials should be brought to room temperature (not to exceed 25°C [77°F]). Vials may remain in the carton at room temperature for up to 6 hours; do not put back into the refrigerator. If not used within 6 hours, they must be discarded.

Once the suspensions have been drawn into the respective syringes, the injections should be administered as soon as possible, but may remain in the syringes for up to 2 hours. The filled syringes should not be placed in the refrigerator. If the medicines remain in the syringes for more than 2 hours, the filled syringes and needles must be discarded [see Dosage and Administration (2.9)].

17 PATIENT COUNSELING INFORMATION

Advise the patient to read the FDA-approved patient labeling (Patient Information).

Hypersensitivity Reactions

Advise patients to immediately contact their healthcare provider if they develop a rash. Instruct patients to immediately stop taking CABENUVA and seek medical attention if they develop a rash associated with any of the following symptoms, as it may be a sign of a more serious reaction such as Stevens-Johnson syndrome (SJS)/toxic epidermal necrolysis (TEN) or drug reaction with eosinophilia and systemic symptoms (DRESS): fever; generally ill feeling; extreme tiredness; muscle or joint aches; blisters; oral blisters or lesions; eye inflammation; facial swelling; swelling of the eyes, lips, tongue, or mouth; difficulty breathing; and/or signs and symptoms of liver problems (e.g., yellowing of the skin or whites of the eyes; dark or tea-colored urine; pale-colored stools or bowel movements; nausea; vomiting; loss of appetite; or pain, aching, or sensitivity on the right side below the ribs). Advise patients that if hypersensitivity occurs, they will be closely monitored, laboratory tests will be ordered, and appropriate therapy will be initiated [see Warnings and Precautions (5.1)].

Adverse Reactions Following Injections

Advise patients that injection site reactions have been reported in the majority of patients receiving CABENUVA. These local reactions typically consist of one or more of the following: pain, erythema, tenderness, pruritus, and local swelling. Systemic reactions have also been reported, such as fever, musculoskeletal pain, and sciatica pain [see Adverse Reactions (6.1)]. Serious post-injection reactions were reported within minutes after the injection of rilpivirine, including dyspnea, bronchospasm, agitation, abdominal cramping, rash/urticaria, dizziness, flushing, sweating, oral numbness, changes in blood pressure, and back pain (e.g., back and chest). These events began to resolve within minutes after the injection. Advise patients that they will be observed briefly (approximately 10 minutes) after the injection. If they experience a post-injection reaction, they will be monitored and appropriate treatment administered [see Warnings and Precautions (5.2)].

Hepatotoxicity

Inform patients that hepatotoxicity has been reported with cabotegravir and rilpivirine, components of CABENUVA [see Warnings and Precautions (5.3), Adverse Reactions (6.1)]. Inform patients that monitoring for liver transaminases is recommended.

Depressive Disorders

Inform patients that depressive disorders (including depressed mood, depression, major depression, mood altered, mood swings, unusual mood, negative thoughts, suicidal ideation, suicide attempt) have been reported with at least one of the components of CABENUVA. Advise patients to seek prompt medical evaluation if they experience depressive symptoms [see Warnings and Precautions (5.4), Adverse Reactions (6.1)].

Drug Interactions

Inform patients that CABENUVA may interact with other drugs; therefore, advise patients to report to their healthcare provider the use of any other prescription or nonprescription medication or herbal products, including St. John’s wort. CABENUVA is an extended-release injectable that may be systemically present for 12 months or longer. These residual concentrations are not expected to affect the exposures of antiretroviral drugs that are initiated after discontinuation of CABENUVA [see Contraindications (4), Drug Interactions (7)].

Adherence to CABENUVA

Counsel patients about the importance of continued medication adherence and scheduled visits to help maintain viral suppression and to reduce risk of loss of virologic response and development of resistance [see Dosage and Administration (2.1), Warnings and Precautions (5.6)].

Two Options for Dosing Frequency

Advise the patient that CABENUVA can be injected monthly or every 2 months after oral lead‑in with cabotegravir and rilpivirine to assess tolerability. Discuss the two injection dosing frequency options with the patient prior to starting CABENUVA and decide which injection dosing frequency would be the most appropriate option for the patient [see Dosage and Administration (2.1)].

Missed Dose

Inform patients that CABENUVA can remain in the body for up to 12 months or longer after receiving their last injection. Advise patients that they should contact their healthcare provider if they miss or plan to miss a scheduled injection visit and that oral therapy with VOCABRIA and EDURANT may be used up to 2 months to replace missed injection visits, or any other fully suppressive oral antiretroviral regimen may be used until injections are resumed. Advise patients that if they stop treatment with CABENUVA, they will need to take other medicines to treat their HIV-1 infection [see Dosage and Administration (2.2, 2.8), Warnings and Precautions (5.6)].

Pregnancy Registry

Inform patients that there is an antiretroviral pregnancy registry to monitor fetal outcomes in those exposed to CABENUVA during pregnancy. Patients who are of reproductive potential should be informed of the long duration of exposure of CABENUVA and that there is very limited clinical experience in human pregnancy [see Warnings and Precautions (5.6), Use in Specific Populations (8.1)].

Lactation

Inform individuals with HIV-1 infection that the potential risks of breastfeeding include: (1) HIV-1 transmission (in HIV-1–negative infants), (2) developing viral resistance (in HIV-1–positive infants), and (3) adverse reactions in a breastfed infant similar to those seen in adults [see Use in Specific Populations (8.2)].

CABENUVA and VOCABRIA are trademarks owned by or licensed to the ViiV Healthcare group of companies.

The other brand listed is a trademark owned by or licensed to its respective owner and is not a trademark owned by or licensed to the ViiV Healthcare group of companies. The maker of this brand is not affiliated with and does not endorse the ViiV Healthcare group of companies or its products.

Manufactured for:

ViiV Healthcare

Durham, NC 27701

©2025 ViiV Healthcare group of companies or its licensor.

CBN:11PI

PATIENT INFORMATION

CABENUVA [KAB-en-ew-vah]

(cabotegravir extended-release injectable suspension;
rilpivirine extended-release injectable suspension)

co-packaged for intramuscular use

What is CABENUVA?

CABENUVA is a prescription medicine that is used without other human immunodeficiency virus-1 (HIV-1) medicines to treat HIV-1 infection in people 12 years of age and older who weigh at least 77 pounds (35 kg) to replace their current HIV-1 medicines when their healthcare provider determines that they meet certain requirements.

HIV-1 is the virus that causes acquired immune deficiency syndrome (AIDS).

CABENUVA contains 2 different medicines:

- cabotegravir
- rilpivirine

It is not known if CABENUVA is safe and effective in children younger than 12 years of age or weighing less than 77 pounds (35 kg).

Do not receive CABENUVA if you:

- have ever had an allergic reaction to cabotegravir or rilpivirine.
- are taking any of the following medicines:

- carbamazepine
- oxcarbazepine
- phenobarbital
- phenytoin
- rifabutin

- rifampin
- rifapentine
- dexamethasone (more than a single-dose treatment)
- St John’s wort (Hypericum perforatum)

Before you receive CABENUVA, tell your healthcare provider about all your medical conditions, including if you:

- have ever had a skin rash or an allergic reaction to medicines that contain cabotegravir or rilpivirine.
- have or have had liver problems, including hepatitis B or C infection.
- have or ever had kidney problems.
- have ever had mental health problems.
- are pregnant or plan to become pregnant. It is not known if CABENUVA will harm your unborn baby. CABENUVA can remain in your body for up to 12 months or longer after the last injection. Tell your healthcare provider if you become pregnant during or after treatment with CABENUVA.
Pregnancy Registry. There is a pregnancy registry for those who take CABENUVA during pregnancy. The purpose of this registry is to collect information about the health of you and your baby. Talk to your healthcare provider about how you can take part in this registry.
- are breastfeeding or plan to breastfeed. CABENUVA may pass into your breast milk. Talk to your healthcare provider about the following risks to your baby from breastfeeding during or after treatment with CABENUVA:
  - the HIV-1 virus may pass to your baby if your baby does not have HIV-1 infection.
  - the HIV-1 virus may become harder to treat if your baby has HIV-1 infection.
  - your baby may get side effects from CABENUVA.

Tell your healthcare provider about all the medicines you take, including prescription and over-the-counter medicines, vitamins, and herbal supplements.

Some medicines interact with CABENUVA. Keep a list of your medicines and show it to your healthcare provider and pharmacist when you get a new medicine.

You can ask your healthcare provider or pharmacist for a list of medicines that interact with CABENUVA.

Do not start taking a new medicine without telling your healthcare provider. Your healthcare provider can tell you if it is safe to take CABENUVA with other medicines.

How will I receive CABENUVA?

- Your healthcare provider will inject CABENUVA into the muscle of each side of your buttocks or on the same side of your buttocks at least 2 cm apart.
- You will receive CABENUVA as 2 injections (cabotegravir and rilpivirine), either one time every month or one time every 2 months.
- Before receiving your first injection doses of CABENUVA, your healthcare provider may have you take 1 VOCABRIA (cabotegravir) tablet and 1 EDURANT (rilpivirine) tablet 1 time a day for 1 month (at least 28 days). This will allow your healthcare provider to assess how well you tolerate these medicines.
- CABENUVA is a long-acting medicine and may stay in your system for 12 months or longer after your last injection.
- Stay under the care of a healthcare provider during treatment with CABENUVA. It is important that you attend your planned appointments to receive your injection doses of CABENUVA.
- If you miss or plan to miss a scheduled monthly or every-2-month injection of CABENUVA by more than 7 days, call your healthcare provider right away to discuss your treatment options.
- If you stop treatment with CABENUVA you will need to take other medicines to treat your HIV-1 infection and reduce the risk of developing viral resistance. Call your healthcare provider right away to discuss your treatment options.

What are the possible side effects of CABENUVA?

CABENUVA may cause serious side effects including:

- Allergic reactions. Call your healthcare provider right away if you develop a rash with CABENUVA. Stop receiving CABENUVA and get medical help right away if you develop a rash with any of the following signs or symptoms:

- fever
- generally ill feeling
- tiredness
- muscle or joint aches
- trouble breathing

- blisters or sores in mouth
- blisters
- redness or swelling of the eyes
- swelling of the mouth, face, lips, or tongue

- Post-injection reactions. Post-injection reaction symptoms have happened within minutes in some people after receiving their rilpivirine injection. Most symptoms resolved within minutes after the injection. Symptoms of post-injection reactions may include:

- trouble breathing
- narrowing of airways
- stomach cramps
- sweating
- numbness of your mouth
- pain (e.g., back and chest)

- feeling anxious
- feeling warm
- rash
- feeling lightheaded or feeling like you are going to pass out (faint)
- blood pressure changes

- Liver problems. Liver problems have happened in people with or without history of liver problems or other risk factors. Your healthcare provider may do blood tests to check your liver function. People with a history of liver problems or people who have certain liver function test changes may have an increased risk of developing new or worsening changes in certain liver tests during treatment with CABENUVA.
Call your healthcare provider right away if you develop any of the following signs or symptoms of liver problems:

- your skin or the white part of your eyes turns yellow (jaundice)
- dark or “tea-colored” urine
- light-colored stools (bowel movements)
- nausea or vomiting

- loss of appetite
- pain, aching, or tenderness on the right side of your stomach area
- itching

- Depression or mood changes. Call your healthcare provider or get emergency medical help right away if you develop any of the following symptoms:
  - feeling sad or hopeless
  - feeling anxious or restless
  - have thoughts of hurting yourself (suicide) or have tried to hurt yourself

The most common side effects of CABENUVA include:

- pain, tenderness, hardened mass or lump, swelling, redness, itching, bruising, and warmth at the injection site
- fever
- tiredness
- headache

- muscle or bone pain
- nausea
- sleep problems
- dizziness
- rash

These are not all the possible side effects of CABENUVA. Call your doctor for medical advice about side effects. You may report side effects to FDA at 1‑800‑FDA‑1088.

General information about the safe and effective use of CABENUVA.

Medicines are sometimes prescribed for purposes other than those listed in a Patient Information leaflet. You can ask your pharmacist or healthcare provider for information about CABENUVA that is written for health professionals.

What are the ingredients in CABENUVA?

Cabotegravir extended-release injectable suspension:

Active ingredient: cabotegravir

Inactive ingredients: mannitol, polyethylene glycol (PEG) 3350, polysorbate 20, and Water for Injection.

Rilpivirine extended-release injectable suspension:

Active ingredient: rilpivirine

Inactive ingredients: citric acid monohydrate, dextrose to ensure isotonicity, monobasic sodium phosphate, poloxamer 338, sodium hydroxide to adjust pH, and Water for Injection.

Manufactured for:

ViiV Healthcare

Durham, NC 27701

CABENUVA and VOCABRIA are trademarks owned by or licensed to the ViiV Healthcare group of companies.

The other brand listed is a trademark owned by or licensed to its respective owner and is not a trademark owned by or licensed to the ViiV Healthcare group of companies. The maker of this brand is not affiliated with and does not endorse the ViiV Healthcare group of companies or its products.

©2025 ViiV Healthcare group of companies or its licensor.

CBN:8PIL

For more information, go to www.cabenuva.com or call 1-877-844-8872.

This Patient Information has been approved by the U.S. Food and Drug Administration. Revised: 11/2025

INSTRUCTIONS FOR USE

Overview:

A complete dose of CABENUVA requires two injections: 400 mg (2 mL) of cabotegravir and 600 mg (2 mL) of rilpivirine.

Cabotegravir and rilpivirine are suspensions that do not need further dilution or reconstitution.

The preparation steps for both medicines are the same. Carefully follow these instructions when preparing the suspension for injection to avoid leakage.

Cabotegravir and rilpivirine are for gluteal intramuscular use only. Each injection must be administered to separate gluteal intramuscular sites (on opposite sides or at least 2 cm apart).

Note: The ventrogluteal site is recommended. The administration order is not important.

Storage information

Store in refrigerator at 2°C to 8°C (36°F to 46°F).

Do not freeze.

Prior to administration:

- Before preparing the injections, the vials may sit in the carton at room temperature (maximum temperature of 25°C [77°F]) for up to 6 hours; do not put back into the refrigerator. If not used within 6 hours, the medicines must be discarded.
- Once the medicines have been drawn into the syringes, they can remain in the syringes for up to 2 hours before injection. The filled syringes should not be placed in the refrigerator. If the medicines remain in the syringes for more than 2 hours, the filled syringes and needles must be discarded.
- It is recommended to label each syringe with the time that the medicine has been drawn into the syringe if the medicine is not administered immediately.

Your pack contains:

- 1 vial of Cabotegravir
- 1 vial of Rilpivirine
- 2 vial adapters
- 2 syringes
- 2 syringe labels
- 2 injection needles (23 gauge, 1½ inch)

Consider the patient’s build and use medical judgment to select an appropriate injection needle length.

You will also need:

- Non-sterile gloves
- 4 alcohol wipes
- 4 gauze pads
- A suitable sharps container

Preparation:

1. Inspect both vials.

Figure A

- Check that the expiration date has not passed. See Figure A.
- Inspect the vials immediately. If you can see foreign matter, do not use the product.
Note: The Cabotegravir vial has a brown tint to the glass.
Do not use if the expiration date has passed.

2. Wait 15 minutes.

Figure B

- Wait at least 15 minutes before you are ready to give the injection to allow the medicine to come to room temperature. See Figure B.

3. Shake the vial vigorously.

Figure C

- Hold the vial firmly, and vigorously shake for a full 10 seconds. See Figure C.
  Note: Vial preparation order is not important.

4. Inspect suspension.

Figure D

- Invert the vial and confirm the suspension is uniform. It should look uniform. See Figure D.
- If the suspension is not uniform, shake the vial again.
- It is also normal to see small air bubbles.

5. Remove the vial cap.

Figure E

- Remove the cap from the vial. See Figure E.
- Wipe the rubber stopper with an alcohol wipe.
Do not allow anything to touch the rubber stopper after wiping it.

6. Peel open the vial adapter.

Figure F

- Peel off the paper backing from the vial adapter packaging. See Figure F.
Note: Do not remove the adapter from its packaging for the next step. The adapter will not fall out when its packaging is turned upside down.

7. Place vial on flat surface and attach the vial adapter.

Figure G

- Ensure the vial is upright and on a flat surface.
- Press the vial adapter straight down onto the vial, as shown.
- The vial adapter should click securely into place. See Figure G.

8. Lift off the packaging.

Figure H

- Lift off the vial adapter packaging, as shown. See Figure H.

9. Prepare the syringe.

Figure I

- Remove the syringe from its packaging.
- Draw 1 mL of air into the syringe. This will make it easier to draw up the medicine later. See Figure I.

10. Attach the syringe.

Figure J

- Hold the vial adapter and vial firmly, as shown.
- Screw the syringe firmly onto the vial adapter. See Figure J.

11. Press the plunger.

Figure K

- Press the plunger all the way down to push the air into the vial. See Figure K.

12. Slowly draw up the dose.

Figure L

- Invert the syringe and vial and slowly withdraw as much of the medicine as possible into the syringe. There may be more medicine than the dose amount. See Figure L.
Note: Keep the syringe upright to avoid leakage.

13. Unscrew the syringe.

Figure M

- Hold the syringe plunger firmly in place as shown to prevent leakage. It is normal to feel some back pressure.
- Unscrew the syringe from the vial adapter, holding the vial adapter as shown. See Figure M.
Note: Check that the suspension looks uniform and milky white.

14. Attach the needle and affix syringe label.

Figure N

- Peel open the needle packaging part way to expose the needle base.
- Keeping the syringe upright, firmly twist the syringe onto the needle.
- Remove the needle packaging from the needle. See Figure N.
- Write the name of the medicine on the syringe label. Affix the label to the syringe making sure the gradations remain visible.

Injection:

15. Prepare the injection site.

Figure O

Injections must be administered to a gluteal site. See Figure O.

Select from the following areas for the injection:

- Ventrogluteal, as shown (recommended)
- Dorsogluteal, not shown (upper outer quadrant)
Note: For gluteal intramuscular use only.
  Do not inject intravenously.

16. Remove the cap.

Figure P

- Fold the needle guard away from the needle. See Figure P.
- Pull off the injection needle cap.

17. Remove extra liquid from the syringe.

Figure Q

- Hold the syringe with the needle pointing up. Press the plunger to the 2-mL dosing mark to remove extra liquid and any air bubbles. See Figure Q.
Note: Clean the injection site with an alcohol wipe. Allow the skin to air dry before continuing.

18. Stretch the skin.

Figure R

Use the z-track injection technique to minimize medicine leakage from the injection site.

- Firmly drag the skin covering the injection site, displacing it by about an inch (2.5 cm). See Figure R.
- Keep it held in this position for the injection.

19. Insert the needle.

Figure S

- Insert the needle to its full depth, or deep enough to reach the muscle. See Figure S.

20. Inject the dose of medicine.

Figure T

- Still holding the skin stretched – slowly press the plunger all the way down. See Figure T.
- Ensure the syringe is empty.
- Withdraw the needle and release the stretched skin immediately.

21. Assess the injection site.

Figure U

- Apply pressure to the injection site using a gauze pad. See Figure U.
- A small bandage may be used if bleeding occurs.
Do not massage the area.

22. Make the needle safe.

Figure V

- Fold the needle guard over the needle. See Figure V.

Figure W

- Gently apply pressure using a hard surface to lock the needle guard in place.
- The needle guard will make a click when it locks. See Figure W.

After injection:

23. Dispose safely.

Figure X

- Dispose of used needles, syringes, vials, and vial adapters according to local health and safety laws. See Figure X.

Repeat for 2nd medicine.

- If you have not yet injected both medicines, use the same steps for preparation and injection of the other medicine.
- The second medicine must be injected into a separate gluteal intramuscular site (on opposite sides or at least 2 cm apart).

Questions and Answers

1. How long can the medicines be left out of the refrigerator?

It is best to inject the medicines as soon as they reach room temperature. However, the vials may sit in the carton at room temperature (maximum temperature of 25°C [77°F]) for up to 6 hours; do not put back into the refrigerator. If not used within 6 hours, the medicines must be discarded.
2. How long can the medicines be left in the syringes?
It is best to inject the (room temperature) medicines as soon as possible after drawing them up. However, the medicines can remain in the syringes for up to 2 hours before injection. The filled syringes should not be placed in the refrigerator.
If the medicines remain in the syringes for more than 2 hours, the filled syringes and needles must be discarded.
3. Why do I need to inject air into the vials?
Injecting 1 mL of air into the vials makes it easier to draw up the medicines into the syringes. Without the air, some liquid may flow back into the vials unintentionally, leaving less medicine than intended in the syringes.
4. Does the order in which I give the medicines matter?
No, the order is unimportant.
5. Is it safe to warm the vials up to room temperature more quickly?
It is best to let the vials come to room temperature naturally. However, you can use the warmth of your hands to speed up the warm-up time, but make sure the vials do not get above 25°C (77°F).
Do not use any other heating methods.

Manufactured for:

ViiV Healthcare

Durham, NC 27701

Trademarks are owned by or licensed to the ViiV Healthcare group of companies.

©2024 ViiV Healthcare group of companies or its licensor.

CBN:6IFU2

This Instructions for Use has been approved by the U.S. Food and Drug Administration. Revised: 9/2024

Overview:

A complete dose of CABENUVA requires two injections: 600 mg (3 mL) of cabotegravir and 900 mg (3 mL) of rilpivirine.

Cabotegravir and rilpivirine are suspensions that do not need further dilution or reconstitution.

The preparation steps for both medicines are the same. Carefully follow these instructions when preparing the suspension for injection to avoid leakage.

Cabotegravir and rilpivirine are for gluteal intramuscular use only. Each injection must be administered to separate gluteal intramuscular sites (on opposite sides or at least 2 cm apart).

Note: The ventrogluteal site is recommended. The administration order is not important.

Storage information

Store in refrigerator at 2°C to 8°C (36°F to 46°F).

Do not freeze.

Prior to administration:

- Before preparing the injections, the vials may sit in the carton at room temperature (maximum temperature of 25°C [77°F]) for up to 6 hours; do not put back into the refrigerator. If not used within 6 hours, the medicines must be discarded.
- Once the medicines have been drawn into the syringes, they can remain in the syringes for up to 2 hours before injection. The filled syringes should not be placed in the refrigerator. If the medicines remain in the syringes for more than 2 hours, the filled syringes and needles must be discarded.
- It is recommended to label the syringe with each time that the medicine has been drawn into the syringe if the medicine is not administered immediately.

Your pack contains:

- 1 vial of Cabotegravir
- 1 vial of Rilpivirine
- 2 vial adapters
- 2 syringes
- 2 syringe labels
- 2 injection needles (23 gauge, 1½ inch)

Consider the patient’s build and use medical judgment to select an appropriate injection needle length.

You will also need:

- Non-sterile gloves
- 4 alcohol wipes
- 4 gauze pads
- A suitable sharps container

Preparation:

1. Inspect both vials.

Figure A

- Check that the expiration date has not passed. See Figure A.
- Inspect the vials immediately. If you can see foreign matter, do not use the product.
Note: The Cabotegravir vial has a brown tint to the glass.
Do not use if the expiration date has passed.

2. Wait 15 minutes.

Figure B

- Wait at least 15 minutes before you are ready to give the injection to allow the medicine to come to room temperature. See Figure B.

3. Shake the vial vigorously.

Figure C

- Hold the vial firmly, and vigorously shake for a full 10 seconds. See Figure C.
  Note: Vial preparation order is not important.

4. Inspect suspension.

Figure D

- Invert the vial and confirm the suspension is uniform. It should look uniform. See Figure D.
- If the suspension is not uniform, shake the vial again.
- It is also normal to see small air bubbles.

5. Remove the vial cap.

Figure E

- Remove the cap from the vial. See Figure E.
- Wipe the rubber stopper with an alcohol wipe.
Do not allow anything to touch the rubber stopper after wiping it.

6. Peel open the vial adapter.

Figure F

- Peel off the paper backing from the vial adapter packaging. See Figure F.
Note: Do not remove the adapter from its packaging for the next step. The adapter will not fall out when its packaging is turned upside down.

7. Place vial on flat surface and attach the vial adapter.

Figure G

- Ensure the vial is upright and on a flat surface.
- Press the vial adapter straight down onto the vial, as shown.
- The vial adapter should click securely into place. See Figure G.

8. Lift off the packaging.

Figure H

- Lift off the vial adapter packaging, as shown. See Figure H.

9. Prepare the syringe.

Figure I

- Remove the syringe from its packaging.
- Draw 1 mL of air into the syringe. This will make it easier to draw up the medicine later. See Figure I.

10. Attach the syringe.

Figure J

- Hold the vial adapter and vial firmly, as shown.
- Screw the syringe firmly onto the vial adapter. See Figure J.

11. Press the plunger.

Figure K

- Press the plunger all the way down to push the air into the vial. See Figure K.

12. Slowly draw up the dose.

Figure L

- Invert the syringe and vial and slowly withdraw as much of the medicine as possible into the syringe. There may be more medicine than the dose amount. See Figure L.
Note: Keep the syringe upright to avoid leakage.

13. Unscrew the syringe.

Figure M

- Hold the syringe plunger firmly in place as shown to prevent leakage. It is normal to feel some back pressure.
- Unscrew the syringe from the vial adapter, holding the vial adapter as shown. See Figure M.
Note: Check that the suspension looks uniform and milky white.

14. Attach the needle and affix syringe label.

Figure N

- Peel open the needle packaging part way to expose the needle base.
- Keeping the syringe upright, firmly twist the syringe onto the needle.
- Remove the needle packaging from the needle. See Figure N.
- Write the name of the medicine on the syringe label. Affix the label to the syringe making sure the gradations remain visible.

Injection:

15. Prepare the injection site.

Figure O

Injections must be administered to a gluteal site. See Figure O.

Select from the following areas for the injection:

- Ventrogluteal, as shown (recommended)
- Dorsogluteal, not shown (upper outer quadrant)
Note: For gluteal intramuscular use only.
  Do not inject intravenously.

16. Remove the cap.

Figure P

- Fold the needle guard away from the needle. See Figure P.
- Pull off the injection needle cap.

17. Remove extra liquid from the syringe.

Figure Q

- Hold the syringe with the needle pointing up. Press the plunger to the 3-mL dosing mark to remove extra liquid and any air bubbles. See Figure Q.
Note: Clean the injection site with an alcohol wipe. Allow the skin to air dry before continuing.

18. Stretch the skin.

Figure R

Use the z-track injection technique to minimize medicine leakage from the injection site.

- Firmly drag the skin covering the injection site, displacing it by about an inch (2.5 cm). See Figure R.
- Keep it held in this position for the injection.

19. Insert the needle.

Figure S

- Insert the needle to its full depth, or deep enough to reach the muscle. See Figure S.

20. Inject the dose of medicine.

Figure T

- Still holding the skin stretched – slowly press the plunger all the way down. See Figure T.
- Ensure the syringe is empty.
- Withdraw the needle and release the stretched skin immediately.

21. Assess the injection site.

Figure U

- Apply pressure to the injection site using a gauze pad. See Figure U.
- A small bandage may be used if bleeding occurs.
Do not massage the area.

22. Make the needle safe.

Figure V

- Fold the needle guard over the needle. See Figure V.

Figure W

- Gently apply pressure using a hard surface to lock the needle guard in place.
- The needle guard will make a click when it locks. See Figure W.

After injection:

23. Dispose safely.

Figure X

- Dispose of used needles, syringes, vials, and vial adapters according to local health and safety laws. See Figure X.

Repeat for 2nd medicine.

- If you have not yet injected both medicines, use the same steps for preparation and injection of the other medicine.
- The second medicine must be injected into a separate gluteal intramuscular site (on opposite sides or at least 2 cm apart).

Questions and Answers

1. How long can the medicines be left out of the refrigerator?

It is best to inject the medicines as soon as they reach room temperature. However, the vials may sit in the carton at room temperature (maximum temperature of 25°C [77°F]) for up to 6 hours; do not put back into the refrigerator. If not used within 6 hours, the medicines must be discarded.
2. How long can the medicines be left in the syringes?
It is best to inject the (room temperature) medicines as soon as possible after drawing them up. However, the medicines can remain in the syringes for up to 2 hours before injection. The filled syringes should not be placed in the refrigerator.
If the medicines remain in the syringes for more than 2 hours, the filled syringes and needles must be discarded.
3. Why do I need to inject air into the vials?
Injecting 1 mL of air into the vials makes it easier to draw up the medicines into the syringes. Without the air, some liquid may flow back into the vials unintentionally, leaving less medicine than intended in the syringes.
4. Does the order in which I give the medicines matter?
No, the order is unimportant.
5. Is it safe to warm the vials up to room temperature more quickly?
It is best to let the vials come to room temperature naturally. However, you can use the warmth of your hands to speed up the warm-up time, but make sure the vials do not get above 25°C (77°F).
Do not use any other heating methods.

Manufactured for:

ViiV Healthcare

Durham, NC 27701

Trademarks are owned by or licensed to the ViiV Healthcare group of companies.

©2024 ViiV Healthcare group of companies or its licensor.

CBN:7IFU3

This Instructions for Use has been approved by the U.S. Food and Drug Administration. Revised: 9/2024

PACKAGE LABEL

PRINCIPAL DISPLAY PANEL

NDC 49702-253-15

CABENUVA

Cabotegravir extended-release

injectable suspension

400 mg/2 mL

(200 mg/mL)

co-packaged with

Rilpivirine extended-release

injectable suspension

600 mg/2 mL

(300 mg/mL)

Rx Only

ViiV Healthcare

For gluteal intramuscular use only.

Healthcare Professional administration only.

Contents:

- 1 Cabotegravir single-dose vial
- 1 Rilpivirine single-dose vial
- 2 Vial adapters
- 2 Syringes
- 2 Injection needles (23 gauge, 1 ½ inch)
- 2 Syringe labels
- Prescribing Information
- Patient Information
- Instructions for Use

Store in refrigerator at 2°C to 8°C (36°F to 46°F).

Do not freeze.

Discard unused portion.

Prior to administration, bring vials to room temperature (not to exceed 25°C (77°F). Vials may remain at room temperature for up to 6 hours. If not used within 6 hours, they must be discarded. Ensure vial adapter is used correctly.

400 mg/600 mg Kit

Cabotegravir – Made in Singapore and Belgium

Rilpivirine – Made in Belgium and Ireland

©2025 ViiV Healthcare group of companies or its licensor.

Rev. 9/25
620000000101118

PACKAGE LABEL

PRINCIPAL DISPLAY PANEL

NDC 49702-240-15

CABENUVA

Cabotegravir extended-release

injectable suspension

600 mg/3 mL

(200 mg/mL)

co-packaged with

Rilpivirine extended-release

injectable suspension

900 mg/3 mL

(300 mg/mL)

Rx Only

ViiV Healthcare

For gluteal intramuscular use only.

Healthcare Professional administration only.

Contents:

- 1 Cabotegravir single-dose vial
- 1 Rilpivirine single-dose vial
- 2 Vial adapters
- 2 Syringes
- 2 Injection needles (23 gauge, 1 ½ inch)
- 2 Syringe labels
- Prescribing Information
- Patient Information
- Instructions for Use

Store in refrigerator at 2°C to 8°C (36°F to 46°F).

Do not freeze.

Discard unused portion.

Prior to administration, bring vials to room temperature (not to exceed 25°C (77°F). Vials may remain at room temperature for up to 6 hours. If not used within 6 hours, they must be discarded. Ensure vial adapter is used correctly.

600 mg/900 mg Kit

Cabotegravir – Made in Singapore and Belgium

Rilpivirine – Made in Belgium and Ireland

©2025 ViiV Healthcare group of companies or its licensor.

Rev. 9/25
620000000101176

PACKAGE LABEL

PRINCIPAL DISPLAY PANEL

NDC 49702-266-63

CABENUVA

Cabotegravir extended-release

injectable suspension

600 mg/3 mL

(200 mg/mL)

co-packaged with

Rilpivirine extended-release

injectable suspension

900 mg/3 mL

(300 mg/mL)

Rx Only

Sample-Not for Sale

ViiV Healthcare

For gluteal intramuscular use only.

Healthcare Professional administration only.

Contents:

- 1 Cabotegravir single-dose vial
- 1 Rilpivirine single-dose vial
- 2 Vial adapters
- 2 Syringes
- 2 Injection needles (23 gauge, 1 ½ inch)
- 2 Syringe labels
- Prescribing Information
- Patient Information
- Instructions for Use

Store in refrigerator at 2°C to 8°C (36°F to 46°F).

Do not freeze.

Discard unused portion.

Prior to administration, bring vials to room temperature (not to exceed 25°C (77°F). Vials may remain at room temperature for up to 6 hours. If not used within 6 hours, they must be discarded. Ensure vial adapter is used correctly.

600 mg/900 mg Kit

Cabotegravir – Made in Singapore and Belgium

Rilpivirine – Made in Belgium and Ireland

©2025 ViiV Healthcare group of companies or its licensor.

Rev. 9/25

62000000010112